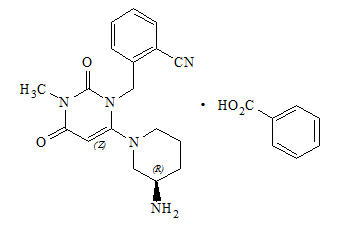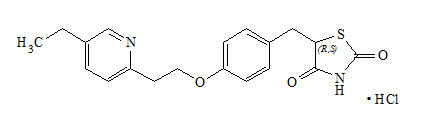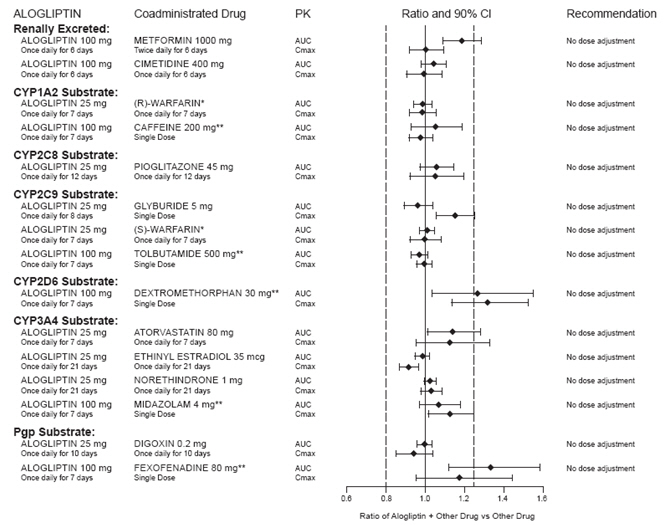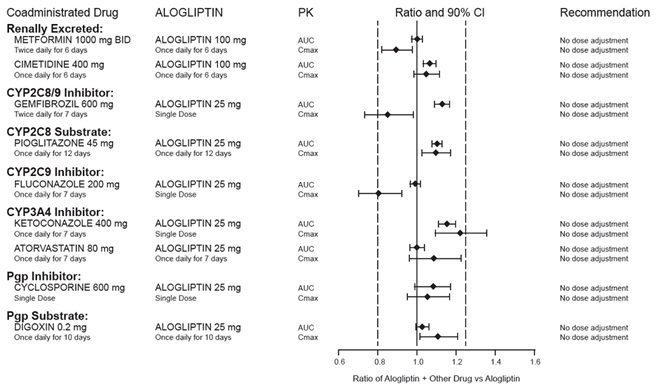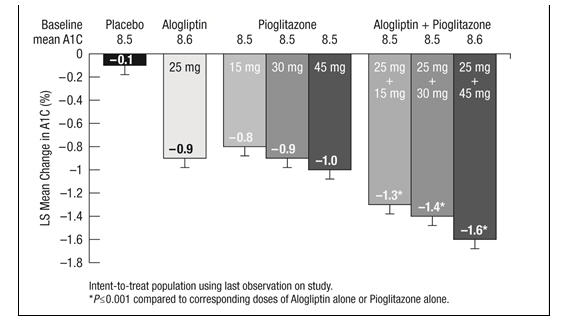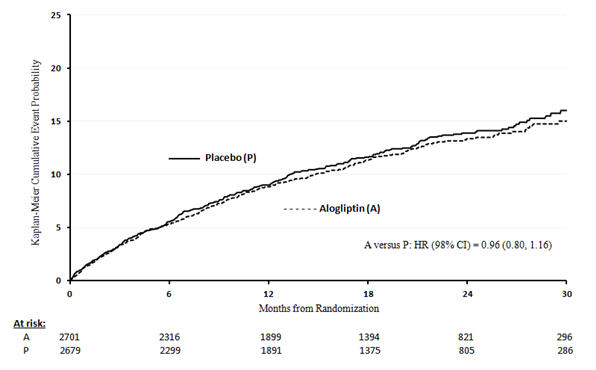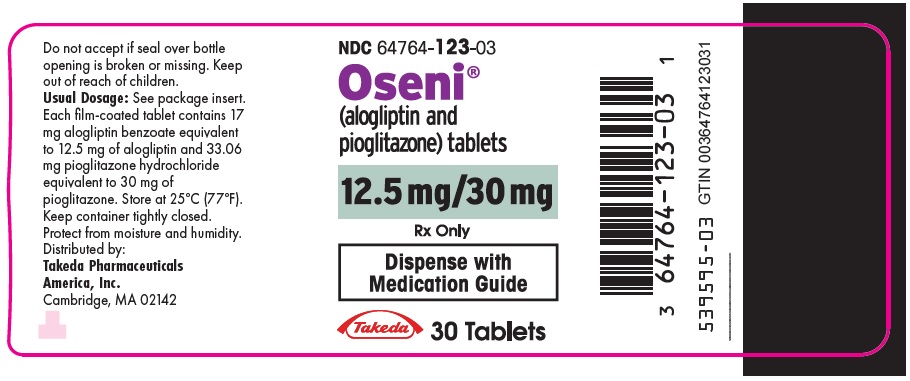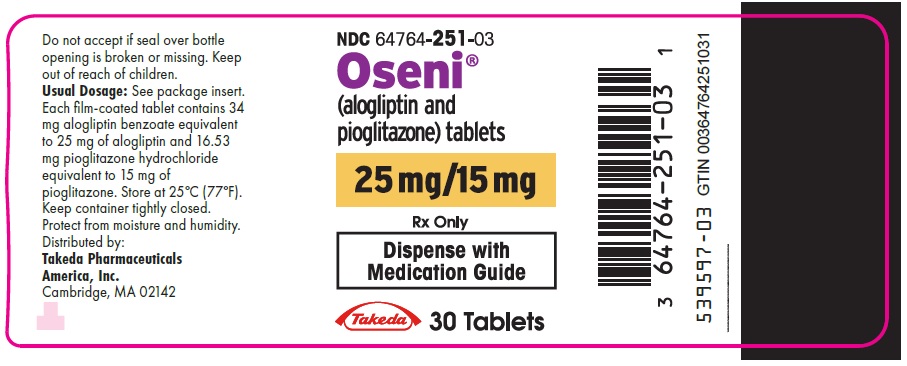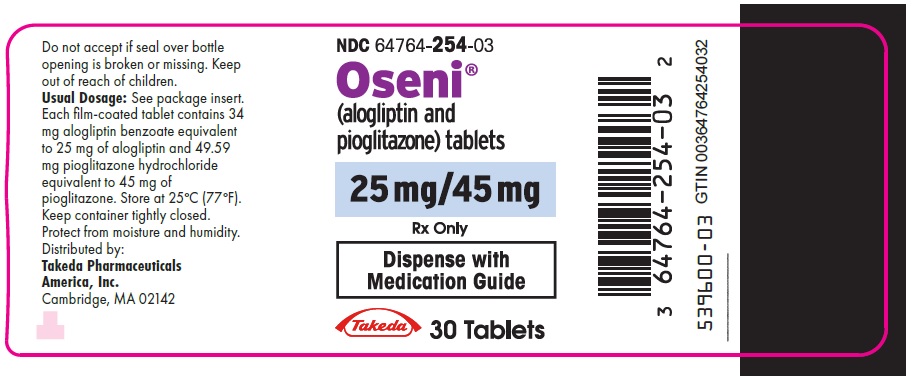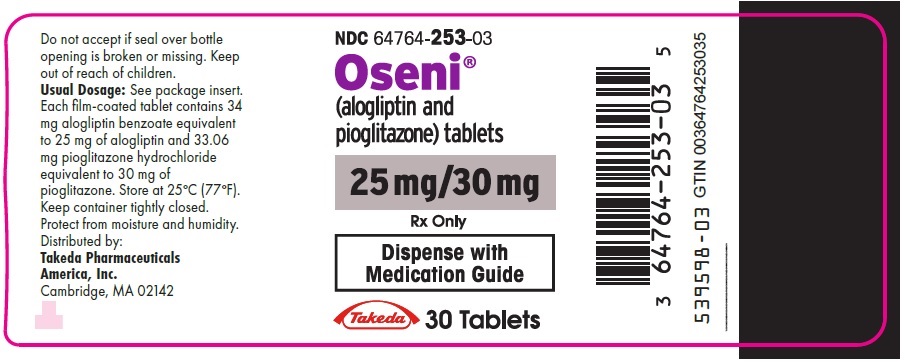 DRUG LABEL: OSENI
NDC: 64764-123 | Form: TABLET, FILM COATED
Manufacturer: Takeda Pharmaceuticals America, Inc.
Category: prescription | Type: HUMAN PRESCRIPTION DRUG LABEL
Date: 20250228

ACTIVE INGREDIENTS: ALOGLIPTIN BENZOATE 12.5 mg/1 1; PIOGLITAZONE HYDROCHLORIDE 30 mg/1 1
INACTIVE INGREDIENTS: MANNITOL; HYDROXYPROPYL CELLULOSE (90000 WAMW); MICROCRYSTALLINE CELLULOSE; CROSCARMELLOSE SODIUM; MAGNESIUM STEARATE; HYPROMELLOSE 2910 (6 MPA.S); TITANIUM DIOXIDE; POLYETHYLENE GLYCOL 8000; TALC; LACTOSE MONOHYDRATE; FERRIC OXIDE YELLOW; FERRIC OXIDE RED; CARNAUBA WAX; POLYGLYCERYL-10 OLEATE; BUTYL ALCOHOL; ALCOHOL; SHELLAC

HIGHLIGHTS OF PRESCRIBING INFORMATION

These highlights do not include all the information needed to use OSENI® safely and effectively. See full prescribing information for OSENI.
OSENI (alogliptin and pioglitazone) tablets, for oral use
Initial U.S. Approval: 2013

WARNING: CONGESTIVE HEART FAILURE

See full prescribing information for complete boxed warning

- Thiazolidinediones, including pioglitazone, which is a component of OSENI, cause or exacerbate congestive heart failure in some patients. (5.1)
- After initiation of OSENI and after dose increases, monitor patients carefully for signs and symptoms of heart failure (e.g., excessive, rapid weight gain, dyspnea and/or edema). If congestive heart failure develops while taking OSENI, consider discontinuation of OSENI or dosage reduction of pioglitazone in OSENI. (5.1)
- OSENI is not recommended in patients with symptomatic heart failure. (5.1)
- Initiation of OSENI in patients with established New York Heart Association (NYHA) Class III or IV heart failure is contraindicated. (4, 5.1)

RECENT MAJOR CHANGES

Dosage and Administration (2.1, 2.2, 2.3, 2.4, 2.5) | 06/2024

1 INDICATIONS AND USAGE

OSENI is a combination of alogliptin, a dipeptidyl peptidase-4 inhibitor, and pioglitazone, a thiazolidinedione agonist of peroxisome proliferator receptor gamma, indicated as an adjunct to diet and exercise to improve glycemic control in adults with type 2 diabetes mellitus. (1)

Limitations of Use: OSENI is not recommended for use in patients with type 1 diabetes mellitus. (1)

2 DOSAGE AND ADMINISTRATION

- Obtain liver tests prior to initiation.
- OSENI may be taken with or without food. (2.1)
- Individualize the starting dose of OSENI based on the patient’s current regimen and concurrent medical condition but do not exceed a daily dose of alogliptin 25 mg and pioglitazone 45 mg. (2.2)
- The recommended starting dosage in patients with NYHA Class I or II congestive heart failure is 25 mg of alogliptin and 15 mg of pioglitazone (2.4)
- Prior to initiation, assess renal function with creatinine clearance (CrCl) (2.3)
  - Mild renal impairment (creatinine clearance [CrCl] ≥60 mL/min): same as the recommended dosage in patients with normal renal function.
  - Moderate renal impairment (CrCl ≥30 to <60 mL/min): 12.5 mg of alogliptin and 30 mg of pioglitazone once daily.
  - Severe renal impairment (CrCl ≥15 to <30 mL/min) or ESRD (CrCl <15 mL/min or requiring hemodialysis): not recommended.

3 DOSAGE FORMS AND STRENGTHS

Tablets:

25 mg alogliptin and 15 mg pioglitazone, 25 mg alogliptin and 30 mg pioglitazone, 25 mg alogliptin and 45 mg pioglitazone. (3)

12.5 mg alogliptin and 30 mg pioglitazone. (3)

4 CONTRAINDICATIONS

- In patients with established NYHA Class III or IV heart failure at the time of OSENI initiation. (4)
- In patients with a history of serious hypersensitivity reaction to alogliptin, pioglitazone, or any of the excipients in OSENI. (4)

5 WARNINGS AND PRECAUTIONS

- Congestive heart failure: Fluid retention may occur and can exacerbate or lead to congestive heart failure. Combination use with insulin and use in congestive heart failure NYHA Class I and II may increase risk. Consider the risks and benefits of OSENI prior to initiating treatment in patients at risk for heart failure. Monitor patients for signs and symptoms. (5.1)
- Pancreatitis: There have been postmarketing reports of acute pancreatitis. If pancreatitis is suspected, promptly discontinue OSENI. (5.2)
- Hypersensitivity: There have been postmarketing reports of serious hypersensitivity reactions in patients treated with alogliptin such as anaphylaxis, angioedema and severe cutaneous adverse reactions, including Stevens-Johnson syndrome. In such cases, promptly discontinue OSENI. (5.3)
- Hepatic effects: Postmarketing reports of hepatic failure, sometimes fatal. Causality cannot be excluded. If liver injury is detected, promptly interrupt OSENI and assess patient for probable cause, then treat cause if possible, to resolution or stabilization. Do not restart OSENI if liver injury is confirmed and no alternative etiology can be found. Use with caution in patients with liver disease. (5.4)
- Edema: Dose-related edema may occur. (5.5)
- Fractures: Increased incidence in female patients. Apply current standards of care for assessing and maintaining bone health. (5.6)
- Urinary bladder tumors: May increase the risk of bladder cancer. Do not use in patients with active bladder cancer. Use caution when using in patients with a prior history of bladder cancer. (5.7)
- Hypoglycemia: Consider a lower dose of insulin or insulin secretagogue to reduce risk of hypoglycemia when used in combination with OSENI. (5.8)
- Macular edema: Postmarketing reports. Recommend regular eye exams in all patients with diabetes according to current standards of care with prompt evaluation for acute visual changes. (5.9)
- Arthralgia: Severe and disabling arthralgia has been reported in patients taking DPP-4 inhibitors. Consider as a possible cause for severe joint pain and discontinue if appropriate. (5.10)
- Bullous pemphigoid: There have been postmarketing reports of bullous pemphigoid requiring hospitalization in patients taking DPP-4 inhibitors. Tell patients to report development of blisters or erosions. If bullous pemphigoid is suspected, discontinue OSENI. (5.11)

6 ADVERSE REACTIONS

The most common adverse reactions (4% or greater incidence) are nasopharyngitis, back pain and upper respiratory tract infection. (6.1)

To report SUSPECTED ADVERSE REACTIONS, contact Takeda Pharmaceuticals America, Inc. at 1-877-TAKEDA-7 (1-877-825-3327) or FDA at 1-800-FDA-1088 or www.fda.gov/medwatch.

7 DRUG INTERACTIONS

- Strong CYP2C8 inhibitors (e.g., gemfibrozil) increase pioglitazone concentrations. Limit the pioglitazone dose to 15 mg daily. (7.2)
- CYP2C8 inducers (e.g., rifampin) may decrease pioglitazone concentrations. (7.3)
- Topiramate may decrease pioglitazone concentrations. (7.4)

8 USE IN SPECIFIC POPULATIONS

- Females and Males of Reproductive Potential: Advise premenopausal females of the potential for an unintended pregnancy. (8.3)
- Pediatrics: safety and effectiveness have not been established. (8.4)

FULL PRESCRIBING INFORMATION

WARNING: CONGESTIVE HEART FAILURE

- Thiazolidinediones, including pioglitazone, which is a component of OSENI®, cause or exacerbate congestive heart failure in some patients [see Warnings and Precautions (5.1)].
- After initiation of OSENI and after dose increases, monitor patients carefully for signs and symptoms of heart failure (e.g., excessive, rapid weight gain, dyspnea and/or edema). If congestive heart failure develops while taking OSENI, consider discontinuation of OSENI or dosage reduction of pioglitazone in OSENI [see Warnings and Precautions (5.1)].
- OSENI is not recommended in patients with symptomatic heart failure [see Warnings and Precautions (5.1)].
- Initiation of OSENI in patients with established New York Heart Association (NYHA) Class III or IV heart failure is contraindicated [see Contraindications (4) and Warnings and Precautions (5.1)].

1 INDICATIONS AND USAGE

OSENI is indicated as an adjunct to diet and exercise to improve glycemic control in adults with type 2 diabetes mellitus.

Limitations of Use

OSENI is not recommended for use in patients with type 1 diabetes mellitus.

2 DOSAGE AND ADMINISTRATION

2.1 Important Dosage and Administration Information

- Obtain liver tests (serum alanine and aspartate aminotransferases, alkaline phosphatase, and total bilirubin) prior to initiating OSENI [see Warnings and Precautions (5.4)].
- Take OSENI orally once daily. Do not split tablets.
- OSENI may be taken with or without food [see Clinical Pharmacology (12.3)].
- If a dose is missed, do not double the next dose.

2.2 Recommended Dosage and Administration

Recommended Starting Dosage Based on Current Regimen

Individualize the starting dosage of OSENI based on the patient's current regimen and the available strengths of OSENI (see Table 1).

Table 1: Recommended Starting Dosage Based on the Patient’s Current Regimen
Current Regimen | Starting Dosage of OSENI (alogliptin/pioglitazone) [For dosage recommendations for patients with renal impairment and/or congestive heart failure, [see Dosage and Administration (2.3, 2.4)].]
Not treated with either alogliptin or pioglitazone | 25 mg/15 mg or 25 mg/30 mg
Alogliptin | 25 mg/15 mg or 25 mg/30 mg
Pioglitazone | 25 mg/15 mg, 25 mg/30 mg, or 25 mg/45 mg
Alogliptin and pioglitazone | Select a dosage that is as close as possible to the current dosage of alogliptin and pioglitazone

Dosage Titration for Additional Glycemic Control

Titrate the OSENI dosage gradually, as needed, after assessing therapeutic response and tolerability, up to a maximum dosage of 25 mg of alogliptin and 45 mg of pioglitazone once daily.

2.3 Recommended Dosage for Patients with Renal Impairment

- Assess renal function prior to initiation of OSENI and periodically thereafter [see Use in Specific Populations (8.6)].
- The recommended dosage of OSENI in patients with mild renal impairment (creatinine clearance [CrCl] ≥60 mL/min) is the same as the recommended dosage in patients with normal renal function [see Dosage and Administration (2.1)].
- The recommended dosage of OSENI for patients with moderate renal impairment (CrCl ≥30 to <60 mL/min) is 12.5 mg of alogliptin and 30 mg of pioglitazone once daily.
- OSENI is not recommended for patients with severe renal impairment (CrCl ≥15 to <30 mL/min) or ESRD (CrCl <15 mL/min or requiring hemodialysis) because these patients require a lower dosage of alogliptin than what is available in the fixed dose combination product, OSENI [see Use in Specific Populations (8.6) and Clinical Pharmacology (12.3)].

2.4 Recommendations for Congestive Heart Failure

Starting Dosage in Patients with NYHA Class I or II Congestive Heart Failure

For patients with preexisting NYHA Class I or II congestive heart failure, the recommended starting dosage of OSENI is 25 mg of alogliptin and 15 mg of pioglitazone [see Boxed Warning and Warnings and Precautions (5.1)].

Monitoring for Fluid Retention and Dosage Modifications for Congestive Heart Failure

After initiation of OSENI or with dosage increase, monitor patients carefully for adverse reactions related to fluid retention as has been seen with pioglitazone (e.g., weight gain, edema and signs and symptoms of congestive heart failure).

If congestive heart failure develops while taking OSENI, consider discontinuation of OSENI or dosage reduction of pioglitazone in OSENI [see Boxed Warning and Warnings and Precautions (5.1)].

2.5 Coadministration with Strong CYP2C8 Inhibitors

The maximum recommended dosage of OSENI is 25 mg of alogliptin and 15 mg of pioglitazone once daily when used in combination with gemfibrozil or other strong CYP2C8 inhibitors [see Drug Interactions (7.1) and Clinical Pharmacology (12.3)].

3 DOSAGE FORMS AND STRENGTHS

Pharmaceutical form | Strength (alogliptin/ pioglitazone) | Color | Shape | Markings (on one side)
film-coated tablets | 12.5 mg/30 mg | Pale peach | Round biconvex | “A/P” and “12.5/30”
film-coated tablets | 25 mg/15 mg | Yellow | Round biconvex | “A/P” and “25/15”
film-coated tablets | 25 mg/30 mg | Peach | Round biconvex | “A/P” and “25/30”
film-coated tablets | 25 mg/45 mg | Red | Round biconvex | “A/P” and “25/45”

4 CONTRAINDICATIONS

OSENI is contraindicated in patients with:

- Established NYHA Class III or IV heart failure at the time of OSENI initiation [see Boxed Warning].
- A history of serious hypersensitivity reaction to alogliptin, pioglitazone, or any of the excipients in OSENI. Reactions such as anaphylaxis, angioedema and severe cutaneous adverse reactions have been reported [see Warnings and Precautions (5.3), Adverse reactions (6.2)].

5 WARNINGS AND PRECAUTIONS

5.1 Congestive Heart Failure

Alogliptin

In the EXAMINE trial which enrolled patients with type 2 diabetes mellitus and recent acute coronary syndrome, 106 (3.9%) of patients treated with alogliptin and 89 (3.3%) of patients treated with placebo were hospitalized for congestive heart failure.

Pioglitazone

Pioglitazone, like other thiazolidinediones, can cause dose-related fluid retention when used alone or in combination with other antidiabetic medications and is most common when pioglitazone is used in combination with insulin. Fluid retention may lead to or exacerbate congestive heart failure [see Boxed Warning, Contraindications (4) and Adverse Reactions (6.1)].

Consider the risks and benefits of OSENI prior to initiating treatment in patients at risk for heart failure, such as those with a prior history of heart failure and a history of renal impairment. Observe these patients for signs and symptoms of congestive heart failure. Advise patients about the symptoms of congestive heart failure and to immediately report such symptoms. If congestive heart failure develops while taking OSENI, consider discontinuation of OSENI or dosage reduction of pioglitazone in OSENI (6.1)].

5.2 Pancreatitis

Acute pancreatitis has been reported in the postmarketing setting and in randomized clinical trials. In glycemic control trials in patients with type 2 diabetes mellitus, acute pancreatitis was reported in 6 (0.2%) patients treated with alogliptin 25 mg and 2 (<0.1%) patients treated with active comparators or placebo. In the EXAMINE trial (a cardiovascular outcomes trial of patients with type 2 diabetes mellitus and high cardiovascular (CV) risk), acute pancreatitis was reported in 10 (0.4%) patients treated with alogliptin and in 7 (0.3%) patients treated with placebo.

It is unknown whether patients with a history of pancreatitis are at increased risk for pancreatitis while using OSENI.

After initiation of OSENI, patients should be observed for signs and symptoms of pancreatitis. If pancreatitis is suspected, OSENI should promptly be discontinued and appropriate management should be initiated.

5.3 Hypersensitivity Reactions

There have been postmarketing reports of serious hypersensitivity reactions in patients treated with alogliptin [see Adverse Reactions (6.2)]. These reactions include anaphylaxis, angioedema and severe cutaneous adverse reactions, including Stevens-Johnson syndrome. If a serious hypersensitivity reaction is suspected, discontinue OSENI, assess for other potential causes for the event and institute alternative treatment for diabetes. Use caution in patients with a history of angioedema with another dipeptidyl peptidase-4 (DPP-4) inhibitor because it is unknown whether such patients will be predisposed to angioedema with OSENI.

5.4 Hepatic Effects

There have been postmarketing reports of fatal and nonfatal hepatic failure in patients taking pioglitazone or alogliptin, although some of the reports contain insufficient information necessary to establish the probable cause [see Adverse Reactions (6.2)].

In glycemic control trials of alogliptin in patients with type 2 diabetes mellitus, serum alanine aminotransferase (ALT) elevations greater than three times the upper limit of normal (ULN) were reported in 1.3% of patients treated with alogliptin 25 mg and 1.7% of patients treated with active comparators or placebo. In the EXAMINE trial (a cardiovascular outcomes trial of patients with type 2 diabetes mellitus and high cardiovascular (CV) risk), increases in serum alanine aminotransferase three times the upper limit of the reference range occurred in 2.4% of patients treated with alogliptin and in 1.8% of patients treated with placebo.

Patients with type 2 diabetes mellitus may have fatty liver disease or cardiac disease with episodic congestive heart failure, both of which may cause liver test abnormalities, and they may also have other forms of liver disease, many of which can be treated or managed. Therefore, obtaining a liver test panel (ALT, aspartate aminotransferase [AST], alkaline phosphatase and total bilirubin) and assessing the patient is recommended before initiating OSENI therapy. In patients with abnormal liver tests, OSENI should be initiated with caution.

Measure liver tests promptly in patients who report symptoms that may indicate liver injury, including fatigue, anorexia, right upper abdominal discomfort, dark urine or jaundice. In this clinical context, if the patient is found to have clinically significant liver enzyme elevations (serum ALT greater than three times the ULN) and if abnormal liver tests persist or worsen, OSENI should be interrupted, and an investigation done to establish the probable cause. OSENI should not be restarted in these patients without another explanation for the liver test abnormalities.

5.5 Edema

In controlled clinical trials, edema was reported more frequently in patients treated with pioglitazone than in placebo-treated patients and is dose-related [see Adverse Reactions (6.1)]. In postmarketing experience, reports of new onset or worsening of edema have been received.

OSENI should be used with caution in patients with edema. Because thiazolidinediones, including pioglitazone, can cause fluid retention, which can exacerbate or lead to congestive heart failure, OSENI should be used with caution in patients at risk for congestive heart failure. Patients treated with OSENI should be monitored for signs and symptoms of congestive heart failure [see Boxed Warning, Warnings and Precautions (5.1)].

5.6 Fractures

In PROactive (the Prospective Pioglitazone Clinical Trial in Macrovascular Events), 5,238 patients with type 2 diabetes mellitus and a history of macrovascular disease were randomized to pioglitazone (N=2,605), force-titrated up to 45 mg daily or placebo (N=2,633) in addition to standard of care. During a mean follow-up of 34.5 months, the incidence of bone fracture in females was 5.1% (44/870) for pioglitazone versus 2.5% (23/905) for placebo. This difference was noted after the first year of treatment and persisted during the course of the study. The majority of fractures observed in female patients were nonvertebral fractures including lower limb and distal upper limb. No increase in the incidence of fracture was observed in men treated with pioglitazone (1.7%) versus placebo (2.1%). The risk of fracture should be considered in the care of patients, especially female patients, treated with pioglitazone and attention should be given to assessing and maintaining bone health according to current standards of care.

5.7 Urinary Bladder Tumors

Tumors were observed in the urinary bladder of male rats in the two-year carcinogenicity study [see Nonclinical Toxicology (13.1)]. In addition, during the three year PROactive clinical trial, 14 patients out of 2,605 (0.54%) randomized to pioglitazone and 5 out of 2,633 (0.19%) randomized to placebo were diagnosed with bladder cancer. After excluding patients in whom exposure to study drug was less than one year at the time of diagnosis of bladder cancer, there were 6 (0.23%) cases on pioglitazone and 2 (0.08%) cases on placebo. After completion of the trial, a large subset of patients was observed for up to 10 additional years, with little additional exposure to pioglitazone. During the 13 years of both PROactive and observational follow-up, the occurrence of bladder cancer did not differ between patients randomized to pioglitazone or placebo [Hazard Ratio (HR) =1.00; (95% Confidence Interval (CI): 0.59, 1.72)].

Findings regarding the risk of bladder cancer in patients exposed to pioglitazone vary among observational studies; some did not find an increased risk of bladder cancer associated with pioglitazone, while others did.

A large prospective 10 year observational cohort study conducted in the United States (U.S.) found no statistically significant increase in the risk of bladder cancer in diabetic patients ever exposed to pioglitazone, compared to those never exposed to pioglitazone [HR = 1.06 (95% CI: 0.89, 1.26)].

A retrospective cohort study conducted with data from the United Kingdom found a statistically significant association between ever exposure to pioglitazone and bladder cancer [HR = 1.63; (95% CI: 1.22, 2.19)].

Associations between cumulative dose or cumulative duration of exposure to pioglitazone and bladder cancer were not detected in some studies including the 10-year observational study in the U.S., but were in others. Inconsistent findings and limitations inherent in these and other studies preclude conclusive interpretations of the observational data.

Pioglitazone may be associated with an increase in the risk of urinary bladder tumors. There are insufficient data to determine whether pioglitazone is a tumor promoter for urinary bladder tumors.

Consequently, OSENI should not be used in patients with active bladder cancer and the benefits of glycemic control versus unknown risks for cancer recurrence with OSENI should be considered in patients with a prior history of bladder cancer.

5.8 Hypoglycemia with Concomitant Use with Insulin or Insulin Secretagogues

Insulin and insulin secretagogues, such as sulfonylureas, are known to cause hypoglycemia. Therefore, a lower dosage of insulin or insulin secretagogue may be required to minimize the risk of hypoglycemia when used in combination with OSENI [see Drug Interactions (7.1)].

5.9 Macular Edema

Macular edema has been reported in postmarketing experience in diabetic patients who were taking pioglitazone or another thiazolidinedione. Some patients presented with blurred vision or decreased visual acuity, but others were diagnosed on routine ophthalmologic examination.

Most patients had peripheral edema at the time macular edema was diagnosed. Some patients had improvement in their macular edema after discontinuation of their thiazolidinedione.

Patients with diabetes should have regular eye exams by an ophthalmologist according to current standards of care. Patients with diabetes who report any visual symptoms should be promptly referred to an ophthalmologist, regardless of the patient's underlying medications or other physical findings [see Adverse Reactions (6.1)].

5.10 Severe and Disabling Arthralgia

There have been postmarketing reports of severe and disabling arthralgia in patients taking DPP-4 inhibitors. The time to onset of symptoms following initiation of drug therapy varied from one day to years. Patients experienced relief of symptoms upon discontinuation of the medication. A subset of patients experienced a recurrence of symptoms when restarting the same drug or a different DPP-4 inhibitor. Consider DPP-4 inhibitors as a possible cause for severe joint pain and discontinue drug if appropriate.

5.11 Bullous Pemphigoid

Postmarketing cases of bullous pemphigoid requiring hospitalization have been reported with DPP-4 inhibitor use. In reported cases, patients typically recovered with topical or systemic immunosuppressive treatment and discontinuation of the DPP-4 inhibitor. Tell patients to report development of blisters or erosions while receiving OSENI. If bullous pemphigoid is suspected, OSENI should be discontinued and referral to a dermatologist should be considered for diagnosis and appropriate treatment.

6 ADVERSE REACTIONS

The following serious adverse reactions are described below or elsewhere in the prescribing information:

- Congestive Heart Failure [see Boxed Warning and Warnings and Precautions (5.1)]
- Pancreatitis [see Warnings and Precautions (5.2)]
- Hypersensitivity Reactions [see Warnings and Precautions (5.3)]
- Hepatic Effects [see Warnings and Precautions (5.4)]
- Edema [see Warnings and Precautions (5.5)]
- Fractures [see Warnings and Precautions (5.6)]
- Urinary Bladder Tumors [see Warnings and Precautions (5.7)]
- Hypoglycemia with Concomitant Use with Insulin or Insulin Secretagogues [see Warnings and Precautions (5.8)]
- Macular Edema [see Warnings and Precautions (5.9)]
- Severe and Disabling Arthralgia [see Warnings and Precautions (5.10)]
- Bullous Pemphigoid [see Warnings and Precautions (5.11)]

6.1 Clinical Trials Experience

Because clinical trials are conducted under widely varying conditions, adverse reaction rates observed in the clinical trials of a drug cannot be directly compared to rates in the clinical trials of another drug and may not reflect the rates observed in practice.

Alogliptin and Pioglitazone

Over 1,500 patients with type 2 diabetes mellitus have received alogliptin coadministered with pioglitazone in four large, randomized, double-blind, controlled clinical trials [see Clinical Studies (14)]. The mean exposure to alogliptin and pioglitazone was 29 weeks with more than 100 subjects treated for more than one year. The studies consisted of two placebo-controlled studies of 16 to 26 weeks in duration and two active-controlled studies of 26 weeks and 52 weeks in duration. In the alogliptin and pioglitazone arm, the mean duration of diabetes was approximately six years, the mean body mass index (BMI) was 31 kg/m^2 (54% of patients had a BMI ≥30 kg/m^2), and the mean age was 54 years (16% of patients ≥65 years of age).

In a pooled analysis of these four controlled clinical studies, the overall incidence of adverse reactions was 65% in patients treated with alogliptin and pioglitazone compared to 57% treated with placebo. Overall discontinuation of therapy due to adverse reactions was 2.5% with alogliptin and pioglitazone compared to 2.0% with placebo, 3.7% with pioglitazone or 1.3% with alogliptin.

Adverse reactions reported in ≥4% of patients treated with alogliptin and pioglitazone and more frequently than in patients who received alogliptin, pioglitazone or placebo are summarized in Table 2.

Table 2. Adverse Reactions Reported in ≥4% of Patients Treated with Alogliptin and Pioglitazone and More Frequently than in Patients Receiving Either Alogliptin, Pioglitazone or Placebo
Number of Patients (%)
 | Alogliptin and pioglitazone [Alogliptin and pioglitazone – includes data pooled for patients receiving alogliptin 25 mg and 12.5 mg combined with pioglitazone 15 mg, 30 mg and 45 mg] | Alogliptin [Alogliptin – includes data pooled for patients receiving alogliptin 25 mg and 12.5 mg] | Pioglitazone [Pioglitazone – includes data pooled for patients receiving pioglitazone 15 mg, 30 mg and 45 mg] | Placebo
 | N=1533 | N=446 | N=949 | N=153
Nasopharyngitis | 75 (4.9) | 21 (4.7) | 37 (3.9) | 6 (3.9)
Back Pain | 64 (4.2) | 9 (2.0) | 32 (3.4) | 5 (3.3)
Upper Respiratory Tract Infection | 63 (4.1) | 19 (4.3) | 26 (2.7) | 5 (3.3)

Alogliptin Add-On Therapy to a Thiazolidinedione

In a 26 week, placebo-controlled, double-blind study, patients inadequately controlled on a thiazolidinedione alone or in combination with metformin or a sulfonylurea were treated with add-on alogliptin therapy or placebo; the adverse reactions reported in ≥5% of patients and more frequently than in patients who received placebo was influenza (alogliptin, 5.5%; placebo, 4.1%).

Hypoglycemia

In a 26 week, placebo-controlled factorial study with alogliptin in combination with pioglitazone on background therapy with metformin, the incidence of subjects reporting hypoglycemia was 0.8%, 0% and 3.8% for alogliptin 25 mg with pioglitazone 15 mg, 30 mg or 45 mg, respectively; 2.3% for alogliptin 25 mg; 4.7%, 0.8% and 0.8% for pioglitazone 15 mg, 30 mg or 45 mg, respectively; and 0.8% for placebo.

In a 26 week, active-controlled, double-blind study with alogliptin alone, pioglitazone alone or alogliptin coadministered with pioglitazone in patients inadequately controlled on diet and exercise, the incidence of hypoglycemia was 3% on alogliptin 25 mg with pioglitazone 30 mg, 0.6% on alogliptin 25 mg and 1.8% on pioglitazone 30 mg.

In a 52 week, active-controlled, double-blind study of alogliptin as add-on therapy to the combination of pioglitazone 30 mg and metformin compared to the titration of pioglitazone 30 mg to 45 mg and metformin, the incidence of subjects reporting hypoglycemia was 4.5% in the alogliptin 25 mg with pioglitazone 30 mg and metformin group versus 1.5% in the pioglitazone 45 mg and metformin group.

Alogliptin

A total of 14,778 patients with type 2 diabetes mellitus participated in 14 randomized, double-blind, controlled clinical trials of whom 9,052 subjects were treated with alogliptin, 3,469 subjects were treated with placebo and 2,257 were treated with an active comparator. The racial distribution of patients exposed to trial medication was 71% White, 17% Asian, 6% Black or African American, 2% American Indian or Alaska Native, 0% Native Hawaiian/Other Pacific Islander and 5% Multiracial or other racial groups. The ethnic distribution was 30% Hispanic or Latino and 70% was not Hispanic or Latino. The mean duration of diabetes was seven years, the mean body mass index (BMI) was 31 kg/m^2 (49% of patients had a BMI ≥30 kg/m^2) and the mean age was 58 years (26% of patients ≥65 years of age).

The mean exposure to alogliptin was 49 weeks with 3,348 subjects treated for more than one year.

In a pooled analysis of these 14 controlled clinical trials, the overall incidence of adverse reactions was 73% in patients treated with alogliptin 25 mg compared to 75% with placebo and 70% with active comparator. Overall discontinuation of therapy due to adverse reactions was 6.8% with alogliptin 25 mg compared to 8.4% with placebo or 6.2% with active comparator.

Adverse reactions reported in ≥4% of adult patients treated with alogliptin 25 mg and more frequently than in patients who received placebo are summarized in Table 3.

Table 3. Adverse Reactions Reported in ≥4% Adult Patients with Type 2 Diabetes Mellitus Treated with Alogliptin 25 mg and More Frequently Than in Patients Given Placebo in Pooled Trials
 | Number of Patients (%)
 | Alogliptin 25 mg | Placebo | Active Comparator
 | N=6447 | N=3469 | N=2257
Nasopharyngitis | 309 (5) | 152 (4) | 113 (5)
Upper Respiratory Tract Infection | 287 (5) | 121 (4) | 113 (5)
Headache | 278 (4) | 101 (3) | 121 (5)

Hypoglycemia

Hypoglycemic events were documented based upon a blood glucose value and/or clinical signs and symptoms of hypoglycemia.

In the monotherapy trial, the incidence of hypoglycemia was 1.5% in patients treated with alogliptin compared to 1.6% with placebo. The use of alogliptin as add-on therapy to glyburide or insulin did not increase the incidence of hypoglycemia compared to placebo. In a monotherapy trial comparing alogliptin to a sulfonylurea in elderly patients, the incidence of hypoglycemia was 5.4% with alogliptin compared to 26% with glipizide.

In the EXAMINE trial, the incidence of investigator reported hypoglycemia was 6.7% in patients receiving alogliptin and 6.5% in patients receiving placebo. Serious adverse reactions of hypoglycemia were reported in 0.8% of patients treated with alogliptin and in 0.6% of patients treated with placebo.

Renal Impairment

In glycemic control trials in patients with type 2 diabetes mellitus, 3.4% of patients treated with alogliptin and 1.3% of patients treated with placebo had renal function adverse reactions. The most commonly reported adverse reactions were renal impairment (0.5% for alogliptin and 0.1% for active comparators or placebo), decreased creatinine clearance (1.6% for alogliptin and 0.5% for active comparators or placebo) and increased blood creatinine (0.5% for alogliptin and 0.3% for active comparators or placebo) [see Use in Specific Populations (8.6)].

In the EXAMINE trial of high CV risk type 2 diabetes mellitus patients, 23% of patients treated with alogliptin and 21% of patients treated with placebo had an investigator reported renal impairment adverse reaction. The most commonly reported adverse reactions were renal impairment (7.7% for alogliptin and 6.7% for placebo), decreased glomerular filtration rate (4.9% for alogliptin and 4.3% for placebo) and decreased renal clearance (2.2% for alogliptin and 1.8% for placebo). Laboratory measures of renal function were also assessed. Estimated glomerular filtration rate decreased by 25% or more in 21.1% of patients treated with alogliptin and 18.7% of patients treated with placebo. Worsening of chronic kidney disease stage was seen in 16.8% of patients treated with alogliptin and in 15.5% of patients treated with placebo.

Pioglitazone

Over 8,500 patients with type 2 diabetes mellitus have been treated with pioglitazone in randomized, double-blind, controlled clinical trials, including 2,605 patients with type 2 diabetes mellitus and macrovascular disease treated with pioglitazone in the PROactive clinical trial. In these trials, over 6,000 patients have been treated with pioglitazone for six months or longer, over 4,500 patients have been treated with pioglitazone for one year or longer, and over 3,000 patients have been treated with pioglitazone for at least two years.

Common Adverse Reactions: 16 to 26-Week Monotherapy Trials

A summary of the incidence and type of common adverse reactions reported in three pooled 16 to 26 week placebo-controlled monotherapy trials of pioglitazone is provided in Table 4. Terms that are reported represent those that occurred at an incidence of >5% and more commonly in patients treated with pioglitazone than in patients who received placebo. None of these adverse reactions were related to pioglitazone dose.

Table 4. Three Pooled 16 to 26 Week Placebo-Controlled Clinical Trials of Pioglitazone Monotherapy: Adverse Reactions Reported at an Incidence >5% and More Commonly in Patients Treated with Pioglitazone than in Patients Treated with Placebo
% of Patients
 | Placebo N=259 | Pioglitazone N=606
Upper Respiratory Tract Infection | 8.5 | 13.2
Headache | 6.9 | 9.1
Sinusitis | 4.6 | 6.3
Myalgia | 2.7 | 5.4
Pharyngitis | 0.8 | 5.1

Congestive Heart Failure

A summary of the incidence of adverse reactions related to congestive heart failure for the 16 to 24 week add-on to sulfonylurea trials, for the 16 to 24 week add-on to insulin trials, and for the 16 to 24 week add-on to metformin trials were (at least one congestive heart failure, 0.2% to 1.7%; hospitalized due to congestive heart failure, 0.2% to 0.9%). None of the reactions were fatal.

Patients with type 2 diabetes mellitus and NYHA class II or early class III congestive heart failure were randomized to receive 24 weeks of double-blind treatment with either pioglitazone at daily doses of 30 mg to 45 mg (N=262) or glyburide at daily doses of 10 mg to 15 mg (N=256). A summary of the incidence of adverse reactions related to congestive heart failure reported in this study is provided in Table 5.

Table 5. Treatment-Emergent Adverse Reactions of Congestive Heart Failure (CHF) in Patients with NYHA Class II or III Congestive Heart Failure Treated with Pioglitazone or Glyburide
 | Number (%) of Subjects
 | Pioglitazone N=262 | Glyburide N=256
Death due to cardiovascular causes (adjudicated) | 5 (1.9%) | 6 (2.3%)
Overnight hospitalization for worsening CHF (adjudicated) | 26 (9.9%) | 12 (4.7%)
Emergency room visit for CHF (adjudicated) | 4 (1.5%) | 3 (1.2%)
Patients experiencing CHF progression during study | 35 (13.4%) | 21 (8.2%)

Congestive heart failure events leading to hospitalization that occurred during the PROactive trial are summarized in Table 6.

Table 6. Treatment-Emergent Adverse Reactions of Congestive Heart Failure (CHF) in PROactive Trial
 | Number (%) of Patients
 | Placebo N=2,633 | Pioglitazone N=2,605
At least one hospitalized congestive heart failure event | 108 (4.1%) | 149 (5.7%)
Fatal | 22 (0.8%) | 25 (1%)
Hospitalized, nonfatal | 86 (3.3%) | 124 (4.7%)

Cardiovascular Safety

In the PROactive trial, 5,238 patients with type 2 diabetes mellitus and a history of macrovascular disease were randomized to pioglitazone (N=2,605), force-titrated up to 45 mg daily or placebo (N=2,633) in addition to standard of care. Almost all patients (95%) were receiving cardiovascular medications (beta blockers, ACE inhibitors, angiotensin II receptor blockers, calcium channel blockers, nitrates, diuretics, aspirin, statins and fibrates). At baseline, patients had a mean age of 62 years, mean duration of diabetes mellitus of 9.5 years and mean A1C of 8.1%. Mean duration of follow-up was 34.5 months.

The primary objective of this trial was to examine the effect of pioglitazone on mortality and macrovascular morbidity in patients with type 2 diabetes mellitus who were at high risk for macrovascular events. The primary efficacy variable was the time to the first occurrence of any event in a cardiovascular composite endpoint that included all-cause mortality, nonfatal myocardial infarction (MI) including silent MI, stroke, acute coronary syndrome, cardiac intervention including coronary artery bypass grafting or percutaneous intervention, major leg amputation above the ankle and bypass surgery or revascularization in the leg. A total of 514 (19.7%) patients treated with pioglitazone and 572 (21.7%) placebo-treated patients experienced at least one event from the primary composite endpoint (hazard ratio = 0.90; 95% Confidence Interval: 0.80, 1.02; p=0.10).

Although there was no statistically significant difference between pioglitazone and placebo for the three-year incidence of a first event within this composite, there was no increase in mortality or in total macrovascular events with pioglitazone. The number of first occurrences and total individual events contributing to the primary composite endpoint is shown in Table 7.

Table 7. PROactive: Number of First and Total Events for Each Component Within the Cardiovascular Composite Endpoint
Cardiovascular Events | Placebo N=2,633 |  | Pioglitazone N=2,605
Cardiovascular Events | First Events n (%) | Total Events n | First Events n (%) | Total Events n
Any Event | 572 (21.7) | 900 | 514 (19.7) | 803
All-Cause Mortality | 122 (4.6) | 186 | 110 (4.2) | 177
Nonfatal Myocardial Infarction (MI) | 118 (4.5) | 157 | 105 (4) | 131
Stroke | 96 (3.6) | 119 | 76 (2.9) | 92
Acute Coronary Syndrome | 63 (2.4) | 78 | 42 (1.6) | 65
Cardiac Intervention (CABG/PCI) | 101 (3.8) | 240 | 101 (3.9) | 195
Major Leg Amputation | 15 (0.6) | 28 | 9 (0.3) | 28
Leg Revascularization | 57 (2.2) | 92 | 71 (2.7) | 115
CABG=coronary artery bypass grafting; PCI=percutaneous intervention

Weight Gain

Dose-related weight gain occurs when pioglitazone is used alone or in combination with other antidiabetic medications. The mechanism of weight gain is unclear but probably involves a combination of fluid retention and fat accumulation.

Edema

Edema induced from taking pioglitazone is reversible when pioglitazone is discontinued. The edema usually does not require hospitalization unless there is coexisting congestive heart failure.

Hepatic Effects

There has been no evidence of pioglitazone-induced hepatotoxicity in the pioglitazone controlled clinical trial database to date. One randomized, double-blind, three-year trial comparing pioglitazone to glyburide as add-on to metformin and insulin therapy was specifically designed to evaluate the incidence of serum ALT elevation to greater than three times the upper limit of the reference range, measured every eight weeks for the first 48 weeks of the trial then every 12 weeks thereafter. A total of 3/1051 (0.3%) patients treated with pioglitazone and 9/1046 (0.9%) patients treated with glyburide developed ALT values greater than three times the upper limit of the reference range. None of the patients treated with pioglitazone in the pioglitazone controlled clinical trial database to date have had a serum ALT greater than three times the upper limit of the reference range and a corresponding total bilirubin greater than two times the upper limit of the reference range, a combination predictive of the potential for severe drug-induced liver injury.

Hypoglycemia

In the pioglitazone clinical trials, adverse reactions of hypoglycemia were reported based on clinical judgment of the investigators and did not require confirmation with finger stick glucose testing.

In the 16-week add-on to sulfonylurea trial, the incidence of reported hypoglycemia was 3.7% with pioglitazone 30 mg and 0.5% with placebo. In the 16-week add-on to insulin trial, the incidence of reported hypoglycemia was 7.9% with pioglitazone 15 mg, 15.4% with pioglitazone 30 mg and 4.8% with placebo.

The incidence of reported hypoglycemia was higher with pioglitazone 45 mg compared to pioglitazone 30 mg in both the 24-week add-on to sulfonylurea trial (15.7% versus 13.4%) and in the 24 week add-on to insulin trial (47.8% versus 43.5%).

Three patients in these four trials were hospitalized due to hypoglycemia. All three patients were receiving pioglitazone 30 mg (0.9%) in the 24-week add-on to insulin trial. An additional 14 patients reported severe hypoglycemia (defined as causing considerable interference with patient’s usual activities) that did not require hospitalization. These patients were receiving pioglitazone 45 mg in combination with sulfonylurea (N=2) or pioglitazone 30 mg or 45 mg in combination with insulin (N=12).

Urinary Bladder Tumors

Tumors were observed in the urinary bladder of male rats in the two-year carcinogenicity study [see Nonclinical Toxicology (13.1)]. During the three-year PROactive clinical trial, 14 patients out of 2,605 (0.54%) randomized to pioglitazone and 5 out of 2,633 (0.19%) randomized to placebo were diagnosed with bladder cancer. After excluding patients in whom exposure to study drug was less than one year at the time of diagnosis of bladder cancer, there were 6 (0.23%) cases on pioglitazone and 2 (0.08%) cases on placebo. After completion of the trial, a large subset of patients was observed for up to 10 additional years, with little additional exposure to pioglitazone. During the 13 years of both PROactive and observational follow-up, the occurrence of bladder cancer did not differ between patients randomized to pioglitazone or placebo (HR =1.00; 95% CI: 0.59-1.72) [see Warnings and Precautions (5.7)].

Laboratory Abnormalities

Pioglitazone

Hematologic Effects

Pioglitazone may cause decreases in hemoglobin and hematocrit. In placebo-controlled monotherapy trials, mean hemoglobin values declined by 2% to 4% in patients treated with pioglitazone compared with a mean change in hemoglobin of -1% to +1% in placebo-treated patients. These changes primarily occurred within the first four to 12 weeks of therapy and remained relatively constant thereafter. These changes may be related to increased plasma volume associated with pioglitazone therapy and are not likely to be associated with any clinically significant hematologic effects.

Creatine Phosphokinase

During protocol-specified measurement of serum creatine phosphokinase (CPK) in pioglitazone clinical trials, an isolated elevation in CPK to greater than 10 times the upper limit of the reference range was noted in nine (0.2%) patients treated with pioglitazone (values of 2,150 to 11,400 IU/L) and in no comparator-treated patients. Six of these nine patients continued to receive pioglitazone, two patients were noted to have the CPK elevation on the last day of dosing and one patient discontinued pioglitazone due to the elevation. These elevations resolved without any apparent clinical sequelae. The relationship of these events to pioglitazone therapy is unknown.

6.2 Postmarketing Experience

The following adverse reactions have been identified during the postmarketing use of alogliptin or pioglitazone. Because these reactions are reported voluntarily from a population of uncertain size, it is not always possible to reliably estimate their frequency or establish a causal relationship to drug exposure.

Alogliptin

Gastrointestinal Disorders: acute pancreatitis, diarrhea, constipation, nausea, ileus

Hepatobiliary Disorders: fulminant hepatic failure

Immune System Disorders: hypersensitivity reactions including anaphylaxis

Investigations: hepatic enzyme elevations

Musculoskeletal and Connective Tissue Disorders: severe and disabling arthralgia, rhabdomyolysis

Renal and Urinary Disorders: tubulointerstitial nephritis

Skin and Subcutaneous Tissue Disorders: angioedema, rash, urticaria and severe cutaneous adverse reactions including Stevens-Johnson syndrome, bullous pemphigoid

Pioglitazone

Cardiac Disorders: rapid increases in weight, edema, congestive heart failure both with and without previously known heart disease or concomitant insulin administration

Eye Disorders: New onset or worsening diabetic macular edema with decreased visual acuity

Hepatobiliary Disorders: Fatal and nonfatal hepatic failure

7 DRUG INTERACTIONS

7.1 Insulin Secretagogues and Insulin

Insulin and insulin secretagogues are known to cause hypoglycemia. Coadministration of OSENI with an insulin secretagogue (e.g., sulfonylurea) or insulin may require lower dosages of the insulin secretagogue and insulin to reduce the risk of hypoglycemia [see Warnings and Precautions (5.8)].

7.2 Strong CYP2C8 Inhibitors

An inhibitor of CYP2C8 (e.g., gemfibrozil) significantly increases the exposure (area under the concentration-time curve [AUC]) and half-life of pioglitazone. Therefore, the maximum recommended dosage of OSENI is 25 mg of alogliptin and 15 mg of pioglitazone once daily if used in combination with gemfibrozil or other strong CYP2C8 inhibitors [see Dosage and Administration (2.5) and Clinical Pharmacology (12.3)].

7.3 CYP2C8 Inducers

An inducer of CYP2C8 (e.g., rifampin) may significantly decrease the exposure (AUC) of pioglitazone. Therefore, if an inducer of CYP2C8 is started or stopped during treatment with OSENI, changes in diabetes treatment may be needed based on clinical response without exceeding the maximum recommended daily dose of OSENI (25 mg of alogliptin and 45 mg of pioglitazone) [see Clinical Pharmacology (12.3)].

7.4 Topiramate

A decrease in the exposure of pioglitazone and its active metabolites were noted with concomitant administration of pioglitazone and topiramate [see Clinical Pharmacology (12.3)]. The clinical relevance of this decrease is unknown; however, when OSENI and topiramate are used concomitantly, monitor patients for adequate glycemic control.

8 USE IN SPECIFIC POPULATIONS

8.1 Pregnancy

Risk Summary

Limited data with OSENI in pregnant women are not sufficient to inform a drug-associated risk for major birth defects or miscarriage. There are risks to the mother and fetus associated with poorly controlled diabetes in pregnancy [see Clinical Considerations].

In animal reproduction studies, no adverse developmental effects were observed when pioglitazone was administered to pregnant rats and rabbits during organogenesis at exposures up to 5 and 35 times the 45 mg clinical dose, respectively, based on body surface area. No adverse developmental effects were observed when alogliptin was administered to pregnant rats and rabbits during organogenesis at exposures 180 and 149 times the 25 mg clinical dose, respectively, based on plasma drug exposure (AUC) [see Data].

The estimated background risk of major birth defects is 6-10% in women with pre-gestational diabetes with a HbA1c >7 and has been reported to be as high as 20-25% in women with a HbA1c >10. The estimated background risk of miscarriage for the indicated population is unknown. In the U.S. general population, the estimated background risk of major birth defects and miscarriage in clinically recognized pregnancies is 2-4% and 15-20%, respectively.

Clinical Considerations

Disease-associated Maternal and/or Embryo/Fetal risk

Poorly controlled diabetes in pregnancy increases the maternal risk for diabetic ketoacidosis, pre-eclampsia, spontaneous abortions, preterm delivery, and delivery complications. Poorly controlled diabetes increases the fetal risk for major birth defects, still birth, and macrosomia related morbidity.

Data

Animal Data

Alogliptin and Pioglitazone

Co-administration of 100 mg/kg alogliptin and 40 mg/kg pioglitazone (39 and 10 times the 25 mg and 45 mg clinical doses, respectively, based on body surface area) to pregnant rats during organogenesis slightly augmented pioglitazone-related fetal effects of delayed development and reduced fetal weights but did not result in embryofetal mortality or teratogenicity.

Alogliptin

Alogliptin administered to pregnant rabbits and rats during the period of organogenesis did not cause adverse developmental effects at doses of up to 200 mg/kg and 500 mg/kg, or 149 times and 180 times, the 25 mg clinical dose, respectively, based on plasma drug exposure (AUC). Placental transfer of alogliptin into the fetus was observed following oral dosing to pregnant rats.

No adverse developmental outcomes were observed in offspring when alogliptin was administered to pregnant rats during gestation and lactation at doses up to 250 mg/kg (~95 times the 25 mg clinical dose, based on AUC).

Pioglitazone

Pioglitazone administered to pregnant rats during organogenesis did not cause adverse developmental effects at a dose of 20 mg/kg (~5-times the 45 mg clinical dose), but delayed parturition and reduced embryofetal viability at 40 and 80 mg/kg, or ≥9-times the 45 mg clinical dose, by body surface area. In pregnant rabbits administered pioglitazone during organogenesis, no adverse developmental effects were observed at 80 mg/kg (~35-times the 45 mg clinical dose), but reduced embryofetal viability at 160 mg/kg, or ~69-times the 45 mg clinical dose, by body surface area. When pregnant rats received pioglitazone during late gestation and lactation, delayed postnatal development, attributed to decreased body weight, occurred in offspring at maternal doses of 10 mg/kg and above or ≥2 times the 45 mg clinical dose, by body surface area.

8.2 Lactation

Risk Summary

There is no information regarding the presence of pioglitazone or alogliptin in human milk, the effects on the breastfed infant, or the effects on milk production. Pioglitazone and alogliptin are present in rat milk; however, due to species-specific differences in lactation physiology, animal lactation data may not reliably predict drug levels in human milk. The developmental and health benefits of breastfeeding should be considered along with the mother’s clinical need for OSENI and any potential adverse effects on the breastfed infant from OSENI or from the underlying maternal condition.

8.3 Females and Males of Reproductive Potential

Discuss the potential for unintended pregnancy with premenopausal women as therapy with pioglitazone, like other thiazolidinediones, may result in ovulation in some anovulatory women.

8.4 Pediatric Use

Safety and effectiveness of OSENI in pediatric patients have not been established.

OSENI is not recommended for use in pediatric patients based on adverse effects observed in adults, including fluid retention and congestive heart failure, fractures and urinary bladder tumors [see Warnings and Precautions (5.1, 5.5, 5.6, 5.7)].

8.5 Geriatric Use

Alogliptin and Pioglitazone

Of the total number of patients (N=1,533) in clinical safety and efficacy studies treated with alogliptin and pioglitazone, 248 (16.2%) patients were 65 years and older and 15 (1%) patients were 75 years and older. No overall differences in safety or effectiveness were observed between patients 65 years of age and older and younger adult patients.

Alogliptin

Of the total number of patients (N=9,052) in clinical safety and efficacy studies treated with alogliptin, 2,257 (24.9%) patients were ≥65 years old and 386 (4.3%) patients were ≥75 years old. No overall differences in safety or effectiveness were observed between patients 65 years of age and older and younger adult patients.

Pioglitazone

A total of 92 patients (15.2%) treated with pioglitazone in the three pooled, 16 to 26 week, double-blind, placebo-controlled, monotherapy trials were ≥65 years old and two patients (0.3%) were ≥75 years old. In the two pooled 16 to 24 week add-on to sulfonylurea trials, 201 patients (18.7%) treated with pioglitazone were ≥65 years old and 19 (1.8%) were ≥75 years old. In the two pooled 16 to 24 week add-on to metformin trials, 155 patients (15.5%) treated with pioglitazone were ≥65 years old and 19 (1.9%) were ≥75 years old. In the two pooled 16 to 24 week add-on to insulin trials, 272 patients (25.4%) treated with pioglitazone were ≥65 years old and 22 (2.1%) were ≥75 years old.

In PROactive, 1068 patients (41%) treated with pioglitazone were ≥65 years old and 42 (1.6%) were ≥75 years old.

In pharmacokinetic studies with pioglitazone, no significant differences were observed in pharmacokinetic parameters between elderly and younger patients. These clinical experiences have not identified differences in effectiveness and safety between the elderly (≥65 years) and younger patients although small sample sizes for patients ≥75 years old limit conclusions [see Clinical Pharmacology (12.3)].

8.6 Renal Impairment

Alogliptin

A total of 602 patients with moderate renal impairment (eGFR ≥30 and <60 mL/min/1.73 m^2) and four patients with severe renal impairment/end-stage renal disease (eGFR <30 mL/min/1.73 m^2 or <15 mL/min/1.73 m^2, respectively) at baseline were treated with alogliptin in clinical trials in patients with type 2 diabetes mellitus.

In the EXAMINE trial of high CV risk type 2 diabetes mellitus patients, 694 patients had moderate renal impairment and 78 patients had severe renal impairment or end-stage renal disease at baseline. The recommended dosage of OSENI for patients with moderate renal impairment (CrCl ≥30 to <60 mL/min) is 12.5 mg of alogliptin and 30 mg of pioglitazone once daily. OSENI is not recommended for patients with severe renal impairment (CrCl ≥15 to <30 mL/min) or ESRD (CrCl <15 mL/min or requiring hemodialysis) [see Dosage and Administration (2.3)].

8.7 Hepatic Impairment

Alogliptin

No dosage adjustments are required in patients with mild to moderate hepatic impairment (Child-Pugh Grade A and B)[see Clinical Pharmacology (12.3)]. Alogliptin has not been studied in patients with severe hepatic impairment (Child-Pugh Grade C). Use caution when administering alogliptin to patients with liver disease [see Warnings and Precautions (5.4)].

Pioglitazone

No dosage adjustments are required in patients with hepatic impairment (Child-Pugh Grade B and C) based on insignificant change in systemic exposures (e.g., AUC) compared to subjects with normal hepatic function in a pharmacokinetic study. However, use with caution in patients with liver disease [see Warnings and Precautions (5.4)].

10 OVERDOSAGE

In the event of an overdose, it is reasonable to institute the necessary clinical monitoring and supportive therapy as dictated by the patient's clinical status. Per clinical judgment, it may be reasonable to initiate removal of unabsorbed material from the gastrointestinal tract.

Alogliptin is minimally dialyzable; over a three-hour hemodialysis session, approximately 7% of the drug was removed. Therefore, hemodialysis is unlikely to be beneficial in an overdose situation. It is not known if alogliptin is dialyzable by peritoneal dialysis.

In the event of an overdose, contact the Poison Help Line (1-800-222-1222) or a medical toxicologist for additional overdosage management recommendations.

11 DESCRIPTION

OSENI tablets contain two oral antihyperglycemic drugs used in the management of type 2 diabetes mellitus: alogliptin and pioglitazone.

Alogliptin

Alogliptin is a selective, orally bioavailable inhibitor of the enzymatic activity of dipeptidyl peptidase-4 (DPP-4). Chemically, alogliptin is prepared as a benzoate salt, which is identified as 2-({6-[(3R)-3-aminopiperidin-1-yl]-3-methyl-2,4-dioxo-3,4-dihydropyrimidin-1(2H)-yl}methyl)benzonitrile monobenzoate. It has a molecular formula of C18H21N5O2∙C7H6O2 and a molecular weight of 461.51 daltons. The structural formula is:

Alogliptin benzoate is a white to off-white crystalline powder containing one asymmetric carbon in the aminopiperidine moiety. It is soluble in dimethylsulfoxide, sparingly soluble in water and methanol, slightly soluble in ethanol and very slightly soluble in octanol and isopropyl acetate.

Pioglitazone

Chemically, pioglitazone is prepared as hydrochloride (HCl) salt, which is identified as (±)-5-[[4-[2-(5-ethyl-2-pyridinyl)ethoxy]phenyl]methyl]-2,4-thiazolidinedione monohydrochloride. It has a molecular formula of C19H20N2O3S∙HCl and a molecular weight of 392.90 daltons. The structural formula is:

Pioglitazone HCl is an odorless white crystalline powder that contains one asymmetric carbon in the thiazolidinedione moiety. The synthetic compound is a racemate and the two enantiomers of pioglitazone interconvert in vivo. It is soluble in N,N dimethylformamide, slightly soluble in anhydrous ethanol, very slightly soluble in acetone and acetonitrile, practically insoluble in water and insoluble in ether.

OSENI is available as a fixed-dose combination tablet for oral administration containing 34 mg alogliptin benzoate equivalent to 25 mg alogliptin and any of the following strengths of pioglitazone HCl:

- 16.53 mg pioglitazone HCl equivalent to 15 mg pioglitazone (25 mg/15 mg)
- 33.06 mg pioglitazone HCl equivalent to 30 mg pioglitazone (25 mg/30 mg)
- 49.59 mg pioglitazone HCl equivalent to 45 mg pioglitazone (25 mg/45 mg)

OSENI is also available as a fixed-dose combination tablet for oral administration containing 17 mg alogliptin benzoate equivalent to 12.5 mg alogliptin for the following strength of pioglitazone HCl:

- 33.06 mg pioglitazone HCl equivalent to 30 mg pioglitazone (12.5 mg/30 mg)

OSENI tablets contain the following inactive ingredients: croscarmellose sodium, hydroxypropyl cellulose, lactose monohydrate, magnesium stearate, mannitol, and microcrystalline cellulose; the tablets are film-coated with ferric oxide (yellow and/or red), hypromellose, polyethylene glycol, talc, titanium dioxide, and are marked with printing ink (Red A1 or Gray F1).

12 CLINICAL PHARMACOLOGY

12.1 Mechanism of Action

OSENI combines two antihyperglycemic agents: alogliptin and pioglitazone.

Alogliptin

Increased concentrations of the incretin hormones such as glucagon-like peptide-1 (GLP-1) and glucose-dependent insulinotropic polypeptide (GIP) are released into the bloodstream from the small intestine in response to meals. These hormones cause insulin release from the pancreatic beta cells in a glucose-dependent manner but are inactivated by the dipeptidyl peptidase-4 (DPP-4) enzyme within minutes. GLP-1 also lowers glucagon secretion from pancreatic alpha cells, reducing hepatic glucose production. In patients with type 2 diabetes mellitus, concentrations of GLP-1 are reduced but the insulin response to GLP-1 is preserved. Alogliptin is a DPP-4 inhibitor that slows the inactivation of the incretin hormones, thereby increasing their bloodstream concentrations and reducing fasting and postprandial glucose concentrations in a glucose-dependent manner in patients with type 2 diabetes mellitus. Alogliptin selectively binds to and inhibits DPP-4 but not DPP-8 or DPP-9 activity in vitro at concentrations approximating therapeutic exposures.

Pioglitazone

Pioglitazone is a thiazolidinedione that depends on the presence of insulin for its mechanism of action. Pioglitazone decreases insulin resistance in the periphery and in the liver resulting in increased insulin-dependent glucose disposal and decreased hepatic glucose output. Pioglitazone is not an insulin secretagogue. Pioglitazone is an agonist for peroxisome proliferator-activated receptor-gamma (PPARγ). PPAR receptors are found in tissues important for insulin action such as adipose tissue, skeletal muscle and liver. Activation of PPARγ nuclear receptors modulates the transcription of a number of insulin-responsive genes involved in the control of glucose and lipid metabolism.

In animal models of diabetes, pioglitazone reduces the hyperglycemia, hyperinsulinemia and hypertriglyceridemia characteristic of insulin-resistant states such as type 2 diabetes mellitus. The metabolic changes produced by pioglitazone result in increased responsiveness of insulin-dependent tissues and are observed in numerous animal models of insulin resistance.

Because pioglitazone enhances the effects of circulating insulin (by decreasing insulin resistance), it does not lower blood glucose in animal models that lack endogenous insulin.

12.2 Pharmacodynamics

Alogliptin and Pioglitazone

In a 26 week, randomized, active-controlled study, patients with type 2 diabetes mellitus received alogliptin 25 mg coadministered with pioglitazone 30 mg, alogliptin 12.5 mg coadministered with pioglitazone 30 mg, alogliptin 25 mg alone or pioglitazone 30 mg alone. Patients who were randomized to alogliptin 25 mg with pioglitazone 30 mg achieved a 26.2% decrease in triglyceride levels from a mean baseline of 214.2 mg/dL compared to an 11.5% decrease for alogliptin alone and a 21.8% decrease for pioglitazone alone. In addition, a 14.4% increase in HDL cholesterol levels from a mean baseline of 43.2 mg/dL was also observed for alogliptin 25 mg with pioglitazone 30 mg compared to a 1.9% increase for alogliptin alone and a 13.2% increase for pioglitazone alone. The changes in measures of LDL cholesterol and total cholesterol were similar between alogliptin 25 mg with pioglitazone 30 mg versus alogliptin alone and pioglitazone alone. A similar pattern of lipid effects was observed in a 26 week, placebo-controlled factorial study.

Alogliptin

Single-dose administration of alogliptin to healthy subjects resulted in a peak inhibition of DPP-4 within two to three hours after dosing. The peak inhibition of DPP-4 exceeded 93% across doses of 12.5 mg to 800 mg. Inhibition of DPP-4 remained above 80% at 24 hours for doses greater than or equal to 25 mg. Peak and total exposure over 24 hours to active GLP-1 were three- to four-fold greater with alogliptin (at doses of 25 to 200 mg) than placebo. In a 16 week, double-blind, placebo-controlled study alogliptin 25 mg demonstrated decreases in postprandial glucagon while increasing postprandial active GLP-1 levels compared to placebo over an eight-hour period following a standardized meal. It is unclear how these findings relate to changes in overall glycemic control in patients with type 2 diabetes mellitus. In this study, alogliptin 25 mg demonstrated decreases in two-hour postprandial glucose compared to placebo (-30 mg/dL versus 17 mg/dL respectively).

Multiple-dose administration of alogliptin to patients with type 2 diabetes mellitus also resulted in a peak inhibition of DPP-4 within one to two hours and exceeded 93% across all doses (25 mg, 100 mg and 400 mg) after a single dose and after 14 days of once-daily dosing. At these doses of alogliptin, inhibition of DPP-4 remained above 81% at 24 hours after 14 days of dosing.

Cardiac Electrophysiology

In a randomized, placebo-controlled, four-arm, parallel-group study, 257 subjects were administered either alogliptin 50 mg, alogliptin 400 mg, moxifloxacin 400 mg or placebo once daily for a total of seven days. No increase in corrected QT (QTc) was observed with either dose of alogliptin. At the 400 mg dose, peak alogliptin plasma concentrations were 19-fold higher than the peak concentrations following the maximum recommended clinical dose of 25 mg.

Pioglitazone

Clinical studies demonstrate that pioglitazone improves insulin sensitivity in insulin-resistant patients. Pioglitazone enhances cellular responsiveness to insulin, increases insulin-dependent glucose disposal, and improves hepatic sensitivity to insulin. In patients with type 2 diabetes mellitus, the decreased insulin resistance produced by pioglitazone results in lower plasma glucose concentrations, lower plasma insulin concentrations and lower A1C values. In controlled clinical trials, pioglitazone had an additive effect on glycemic control when used in combination with a sulfonylurea, metformin or insulin [see Clinical Studies (14)].

Patients with lipid abnormalities were included in clinical trials with pioglitazone. Overall, patients treated with pioglitazone had mean decreases in serum triglycerides, mean increases in HDL cholesterol and no consistent mean changes in LDL and total cholesterol. There is no conclusive evidence of macrovascular benefit with pioglitazone [see Warnings and Precautions (5.12) and Adverse Reactions (6.1)].

In a 26 week, placebo-controlled, dose-ranging monotherapy study, mean serum triglycerides decreased in the pioglitazone 15 mg, 30 mg and 45 mg dose groups compared to a mean increase in the placebo group. Mean HDL cholesterol increased to a greater extent in patients treated with pioglitazone than in the placebo-treated patients. There were no consistent differences for LDL and total cholesterol in patients treated with pioglitazone compared to placebo (Table 8).

Table 8. Lipids in a 26 Week, Placebo-Controlled, Monotherapy, Dose-Ranging Study
 | Placebo | Pioglitazone 15 mg Once Daily | Pioglitazone 30 mg Once Daily | Pioglitazone 45 mg Once Daily
Triglycerides (mg/dL) | N=79 | N=79 | N=84 | N=77
Baseline (mean) | 263 | 284 | 261 | 260
Percent change from baseline (adjusted mean [Adjusted for baseline, pooled center and pooled center by treatment interaction]) | 4.8% | -9% [p<0.05 versus placebo] | -9.6% | -9.3%
HDL Cholesterol (mg/dL) | N=79 | N=79 | N=83 | N=77
Baseline (mean) | 42 | 40 | 41 | 41
Percent change from baseline (adjusted mean) | 8.1% | 14.1% | 12.2% | 19.1%
LDL Cholesterol (mg/dL) | N=65 | N=63 | N=74 | N=62
Baseline (mean) | 139 | 132 | 136 | 127
Percent change from baseline (adjusted mean) | 4.8% | 7.2% | 5.2% | 6%
Total Cholesterol (mg/dL) | N=79 | N=79 | N=84 | N=77
Baseline (mean) | 225 | 220 | 223 | 214
Percent change from baseline (adjusted mean) | 4.4% | 4.6% | 3.3% | 6.4%

In the two other monotherapy studies (16 weeks and 24 weeks) and in combination therapy studies with sulfonylurea (16 weeks and 24 weeks), metformin (16 weeks and 24 weeks) or insulin (16 weeks and 24 weeks), the lipid results were generally consistent with the data above.

12.3 Pharmacokinetics

Absorption

Alogliptin and Pioglitazone

In bioequivalence studies of OSENI, the area under the plasma concentration curve (AUC) and maximum concentration (Cmax) of both the alogliptin and the pioglitazone component following a single dose of the combination tablet (12.5 mg/15 mg or 25 mg/45 mg) were bioequivalent to alogliptin (12.5 mg or 25 mg) concomitantly administered with pioglitazone (15 mg or 45 mg respectively) tablets under fasted conditions in healthy subjects.

Administration of OSENI 25 mg/45 mg with food resulted in no significant change in overall exposure of alogliptin or pioglitazone. OSENI may therefore be administered with or without food.

Alogliptin

The absolute bioavailability of alogliptin is approximately 100%. Administration of alogliptin with a high-fat meal results in no significant change in total and peak exposure to alogliptin. Alogliptin may therefore be administered with or without food.

Pioglitazone

Following oral administration of pioglitazone hydrochloride, peak concentrations of pioglitazone were observed within two hours. Food slightly delays the time to peak serum concentration (Tmax) to three to four hours but does not alter the extent of absorption (AUC).

Distribution

Alogliptin

Following a single, 12.5 mg intravenous infusion of alogliptin to healthy subjects, the volume of distribution during the terminal phase was 417 L, indicating that the drug is well distributed into tissues.

Alogliptin is 20% bound to plasma proteins.

Pioglitazone

The mean apparent Vd/F of pioglitazone following single-dose administration is 0.63 ± 0.41 (mean ± SD) L/kg of body weight. Pioglitazone is extensively protein bound (>99%) in human serum, principally to serum albumin. Pioglitazone also binds to other serum proteins, but with lower affinity. Metabolites M-III and M-IV also are extensively bound (>98%) to serum albumin.

Elimination

Metabolism

Alogliptin

Alogliptin does not undergo extensive metabolism and 60% to 71% of the dose is excreted as unchanged drug in the urine.

Two minor metabolites were detected following administration of an oral dose of [^14C] alogliptin, N-demethylated, M-I (less than 1% of the parent compound), and N-acetylated alogliptin, M-II (less than 6% of the parent compound). M-I is an active metabolite and is an inhibitor of DPP-4 similar to the parent molecule; M-II does not display any inhibitory activity toward DPP-4 or other DPP-related enzymes. In vitro data indicate that CYP2D6 and CYP3A4 contribute to the limited metabolism of alogliptin.

Alogliptin exists predominantly as the (R)-enantiomer (more than 99%) and undergoes little or no chiral conversion in vivo to the (S)-enantiomer. The (S)-enantiomer is not detectable at the 25 mg dose.

Pioglitazone

Pioglitazone is extensively metabolized by hydroxylation and oxidation; the metabolites also partly convert to glucuronide or sulfate conjugates. Metabolites M-III and M-IV are the major circulating active metabolites in humans. Following once-daily administration of pioglitazone, steady-state serum concentrations of both pioglitazone and its major active metabolites, M-III (keto derivative of pioglitazone) and M-IV (hydroxyl derivative of pioglitazone), are achieved within seven days. At steady-state, M-III and M-IV reach serum concentrations equal to or greater than that of pioglitazone. At steady-state, in both healthy volunteers and patients with type 2 diabetes mellitus, pioglitazone comprises approximately 30% to 50% of the peak total pioglitazone serum concentrations (pioglitazone plus active metabolites) and 20% to 25% of the total AUC.

Maximum serum concentration (Cmax), AUC and trough serum concentrations (Cmin) for pioglitazone and M-III and M-IV, increased proportionally with administered doses of 15 mg and 30 mg per day.

In vitro data demonstrate that multiple CYP isoforms are involved in the metabolism of pioglitazone. The cytochrome P450 isoforms involved are CYP2C8 and, to a lesser degree, CYP3A4 with additional contributions from a variety of other isoforms, including the mainly extrahepatic CYP1A1. In vivo studies of pioglitazone in combination with gemfibrozil, a strong CYP2C8 inhibitor, showed that pioglitazone is a CYP2C8 substrate [see Dosage and Administration (2.5) and Drug Interactions (7)]. Urinary 6β-hydroxycortisol/cortisol ratios measured in patients treated with pioglitazone showed that pioglitazone is not a strong CYP3A4 enzyme inducer.

Excretion

Alogliptin

The primary route of elimination of [^14C] alogliptin derived radioactivity occurs via renal excretion (76%) with 13% recovered in the feces, achieving a total recovery of 89% of the administered radioactive dose. The renal clearance of alogliptin (9.6 L/hr) indicates some active renal tubular secretion and systemic clearance was 14.0 L/hr.

Pioglitazone

Following oral administration, approximately 15% to 30% of the pioglitazone dose is recovered in the urine. Renal elimination of pioglitazone is negligible, and the drug is excreted primarily as metabolites and their conjugates. It is presumed that most of the oral dose is excreted into the bile either unchanged or as metabolites and eliminated in the feces.

The mean serum half-life of pioglitazone and its metabolites (M-III and M-IV) range from three to seven hours and 16 to 24 hours, respectively. Pioglitazone has an apparent clearance, CL/F, calculated to be 5 to 7 L/hr.

Specific Populations

Geriatric Patients

Alogliptin

No dosage adjustment of alogliptin is necessary based on age. Age did not have any clinically meaningful effect on the pharmacokinetics of alogliptin.

Pioglitazone

In healthy elderly subjects, peak serum concentrations of pioglitazone and total pioglitazone are not significantly different, but AUC values are approximately 21% higher than those achieved in younger subjects. The mean terminal half-life values of pioglitazone were also longer in elderly subjects (about 10 hours) as compared to younger subjects (about seven hours). These changes are not considered clinically relevant.

Pediatric Patients

Alogliptin

Studies characterizing the pharmacokinetics of alogliptin in pediatric patients have not been performed.

Pioglitazone

Safety and efficacy of pioglitazone in pediatric patients have not been established. Pioglitazone is not recommended for use in pediatric patients [see Use in Specific Populations (8.4)].

Male and Female Patients

Alogliptin

No dosage adjustment of alogliptin is necessary based on gender. Gender did not have any clinically meaningful effect on the pharmacokinetics of alogliptin.

Pioglitazone

The mean Cmax and AUC values of pioglitazone were increased 20% to 60% in females compared to males. In controlled clinical trials, A1C decreases from baseline were generally greater for females than for males (mean difference in A1C 0.5%). Because therapy should be individualized for each patient to achieve glycemic control, no dosage adjustment is recommended based on gender alone.

Race and Ethnic Groups

Alogliptin

No dosage adjustment of alogliptin is necessary based on race. Race (White, Black or African American, and Asian) did not have any clinically meaningful effect on the pharmacokinetics of alogliptin.

Pioglitazone

Pharmacokinetic data among various ethnic groups are not available.

Patients with Renal Impairment

Alogliptin

A single-dose, open-label study was conducted to evaluate the pharmacokinetics of alogliptin 50 mg in patients with chronic renal impairment compared with healthy subjects.

In patients with mild renal impairment (creatinine clearance [CrCl] ≥60 to <90 mL/min), an approximate 1.2-fold increase in plasma AUC of alogliptin was observed. Because increases of this magnitude are not considered clinically relevant, dosage adjustment for patients with mild renal impairment is not recommended.

In patients with moderate renal impairment (CrCl ≥30 to <60 mL/min), an approximate two-fold increase in plasma AUC of alogliptin was observed. To maintain similar systemic exposures of OSENI to those with normal renal function, the recommended dosage of OSENI is 12.5 mg/30 mg once daily in patients with moderate renal impairment.

In patients with severe renal impairment (CrCl ≥15 to <30 mL/min) and end-stage renal disease (ESRD) (CrCl <15 mL/min or requiring dialysis), an approximate three- and four-fold increase in plasma AUC of alogliptin were observed, respectively. Dialysis removed approximately 7% of the drug during a three-hour dialysis session. OSENI is not recommended for patients with severe renal impairment or ESRD because these patients require a lower dosage of alogliptin than what is available in the fixed dose combination product, OSENI.

Pioglitazone

The serum elimination half-life of pioglitazone, M-III and M-IV remains unchanged in patients with moderate (creatinine clearance 30 to 50 mL/min) to severe (creatinine clearance <30 mL/min) renal impairment when compared to subjects with normal renal function. Therefore no dosage adjustment in patients with renal impairment is required.

Patients with Hepatic Impairment

Alogliptin

Total exposure to alogliptin was approximately 10% lower and peak exposure was approximately 8% lower in patients with moderate hepatic impairment (Child-Pugh Grade B) compared to healthy subjects. The magnitude of these reductions is not considered to be clinically meaningful. Patients with severe hepatic impairment (Child-Pugh Grade C) have not been studied. Use caution when administering OSENI to patients with liver disease [see Use in Specific Populations (8.7) and Warnings and Precautions (5.4)].

Pioglitazone

Compared with healthy controls, subjects with impaired hepatic function (Child-Pugh Grade B and C) have an approximate 45% reduction in pioglitazone and total pioglitazone (pioglitazone, M-III and M-IV) mean peak concentrations but no change in the mean AUC values. Therefore, no dosage adjustment in patients with hepatic impairment is required.

There are postmarketing reports of liver failure with pioglitazone and clinical trials have generally excluded patients with serum ALT >2.5 times the upper limit of the reference range. Use caution in patients with liver disease [see Warnings and Precautions (5.4)].

Drug Interaction Studies

Coadministration of alogliptin 25 mg once daily with a CYP2C8 substrate, pioglitazone 45 mg once daily for 12 days had no clinically meaningful effects on the pharmacokinetics of pioglitazone and its active metabolites.

Specific pharmacokinetic drug interaction studies with OSENI have not been performed, although such studies have been conducted with the individual components of OSENI (alogliptin and pioglitazone).

Alogliptin

In Vitro Assessment of Drug Interactions

In vitro studies indicate that alogliptin is neither an inducer of CYP1A2, CYP2B6, CYP2C9, CYP2C19 and CYP3A4, nor an inhibitor of CYP1A2, CYP2C8, CYP2C9, CYP2C19, CYP3A4 and CYP2D6 at clinically relevant concentrations.

In Vivo Assessment of Drug Interactions

Effects of Alogliptin on the Pharmacokinetics of Other Drugs

In clinical studies, alogliptin did not meaningfully increase the systemic exposure to the following drugs that are metabolized by CYP isozymes or excreted unchanged in urine (Figure 1). No dosage adjustment of alogliptin is recommended based on results of the described pharmacokinetic studies.

Figure 1. Effect of Alogliptin on the Pharmacokinetic Exposure to Other Drugs

*Warfarin was given once daily at a stable dose in the range of 1 mg to 10 mg. Alogliptin had no significant effect on the prothrombin time (PT) or International Normalized Ratio (INR).

**Caffeine (1A2 substrate), tolbutamide (2C9 substrate), dextromethorphan (2D6 substrate), midazolam (3A4 substrate) and fexofenadine (P-gp substrate) were administered as a cocktail.

Effects of Other Drugs on the Pharmacokinetics of Alogliptin

There are no clinically meaningful changes in the pharmacokinetics of alogliptin when alogliptin is administered concomitantly with the drugs described below (Figure 2).

Figure 2. Effect of Other Drugs on the Pharmacokinetic Exposure of Alogliptin

Pioglitazone

Table 9. Effect of Pioglitazone Coadministration on Systemic Exposure of Other Drugs
 | Coadministered Drug
Pioglitazone Dosage Regimen (mg) [Daily for seven days unless otherwise noted] | Name and Dose Regimens | Change in AUC [% change (with/without coadministered drug and no change=0%); symbols of ↑ and ↓ indicate the exposure increase and decrease, respectively] |  |  | Change in Cmax
45 mg (N=12) | Warfarin [Pioglitazone had no clinically significant effect on prothrombin time]
45 mg (N=12) | Daily loading then maintenance doses based PT and INR values Quick's Value=35 ± 5% | R-Warfarin |  | ↓3% | R-Warfarin |  | ↓2%
45 mg (N=12) | Daily loading then maintenance doses based PT and INR values Quick's Value=35 ± 5% | S-Warfarin |  | ↓1% | S-Warfarin |  | ↑1%
45 mg (N=12) | Digoxin
45 mg (N=12) | 0.200 mg twice daily (loading dose) then 0.250 mg daily (maintenance dose, 7 days) | ↑15% |  |  | ↑17%
45 mg daily for 21 days (N=35) | Oral Contraceptive
45 mg daily for 21 days (N=35) | [Ethinyl Estradiol (EE) 0.035 mg plus Norethindrone (NE) 1 mg] for 21 days | EE | ↓11% |  | EE | ↓13%
45 mg daily for 21 days (N=35) | [Ethinyl Estradiol (EE) 0.035 mg plus Norethindrone (NE) 1 mg] for 21 days | NE | ↑3% |  | NE | ↓7%
45 mg (N=23) | Fexofenadine
45 mg (N=23) | 60 mg twice daily for 7 days | ↑30% |  |  | ↑37%
45 mg (N=14) | Glipizide
45 mg (N=14) | 5 mg daily for 7 days | ↓3% |  |  | ↓8%
45 mg daily for 8 days (N=16) | Metformin
45 mg daily for 8 days (N=16) | 1000 mg single dose on 8 days | ↓3% |  |  | ↓5%
45 mg (N=21) | Midazolam
45 mg (N=21) | 7.5 mg single dose on day 15 | ↓26% |  |  | ↓26%
45 mg (N=24) | Ranitidine
45 mg (N=24) | 150 mg twice daily for 7 days | ↑1% |  |  | ↓1%
45 mg daily for 4 days (N=24) | Nifedipine ER
45 mg daily for 4 days (N=24) | 30 mg daily for 4 days | ↓13% |  |  | ↓17%
45 mg (N=25) | Atorvastatin Calcium
45 mg (N=25) | 80 mg daily for 7 days | ↓14% |  |  | ↓23%
45 mg (N=22) | Theophylline
45 mg (N=22) | 400 mg twice daily for 7 days | ↑2% |  |  | ↑5%

Table 10. Effect of Coadministered Drugs on Pioglitazone Systemic Exposure
Coadministered Drug and Dosage Regimen | Pioglitazone
Coadministered Drug and Dosage Regimen | Dose Regimen (mg) [Daily for seven days unless otherwise noted] | Change in AUC [Mean ratio (with/without coadministered drug and no change=one-fold) % change (with/without coadministered drug and no change=0%); symbols of ↑ and ↓ indicate the exposure increase and decrease, respectively] | Change in Cmax
Gemfibrozil 600 mg twice daily for 2 days (N=12) | 30 mg single dose | ↑3.4-fold [The half-life of pioglitazone increased from 6.5 hours to 15.1 hours in the presence of gemfibrozil [see Dosage and Administration (2.5) and Drug Interactions (7)]] | ↑6%
Ketoconazole 200 mg twice daily for 7 days (N=28) | 45 mg | ↑34% | ↑14%
Rifampin 600 mg daily for 5 days (N=10) | 30 mg single dose | ↓54% | ↓5%
Fexofenadine 60 mg twice daily for 7 days (N=23) | 45 mg | ↑1% | 0%
Ranitidine 150 mg twice daily for 4 days (N=23) | 45 mg | ↓13% | ↓16%
Nifedipine ER 30 mg daily for 7 days (N=23) | 45 mg | ↑5% | ↑4%
Atorvastatin Calcium 80 mg daily for 7 days (N=24) | 45 mg | ↓24% | ↓31%
Theophylline 400 mg twice daily for 7 days (N=22) | 45 mg | ↓4% | ↓2%
Topiramate 96 mg twice daily for 7 days [Indicates duration of concomitant administration with highest twice-daily dose of topiramate from Day 14 onwards over the 22 days of study] (N=26) | 30 mg | ↓15% [Additional decrease in active metabolites; 60% for M-III and 16% for M-IV] | 0%

13 NONCLINICAL TOXICOLOGY

13.1 Carcinogenesis, Mutagenesis, Impairment of Fertility

Alogliptin and Pioglitazone

No carcinogenicity, mutagenicity or impairment of fertility studies have been conducted with OSENI. The following data are based on findings in studies performed with alogliptin or pioglitazone individually.

Alogliptin

Rats were administered oral doses of 75, 400 and 800 mg/kg alogliptin for two years. No drug-related tumors were observed up to 75 mg/kg or approximately 32 times the maximum recommended clinical dose of 25 mg, based on area under the plasma concentration curve (AUC) exposure. At higher doses (approximately 308 times the maximum recommended clinical dose of 25 mg), a combination of thyroid C-cell adenomas and carcinomas increased in male but not female rats. No drug-related tumors were observed in mice after administration of 50, 150 or 300 mg/kg alogliptin for two years, or up to approximately 51 times the maximum recommended clinical dose of 25 mg, based on AUC exposure.

Alogliptin was not mutagenic or clastogenic, with and without metabolic activation, in the Ames test with S. typhimurium and E. coli or the cytogenetic assay in mouse lymphoma cells. Alogliptin was negative in the in vivo mouse micronucleus study.

In a fertility study in rats, alogliptin had no adverse effects on early embryonic development, mating or fertility at doses up to 500 mg/kg, or approximately 172 times the clinical dose based on plasma drug exposure (AUC).

Pioglitazone

A two-year carcinogenicity study was conducted in male and female rats at oral doses up to 63 mg/kg (approximately 14 times the MRHD of 45 mg based on mg/m^2). Drug-induced tumors were not observed in any organ except for the urinary bladder. Benign and/or malignant transitional cell neoplasms were observed in male rats at 4 mg/kg and above (approximately equal to the MRHD based on mg/m^2). A two-year carcinogenicity study was conducted in male and female mice at oral doses up to 100 mg/kg (approximately 11 times the MRHD based on mg/m^2). No drug-induced tumors were observed in any organ.

Pioglitazone was not mutagenic in a battery of genetic toxicology studies, including the Ames bacterial assay, a mammalian cell forward gene mutation assay (CHO/HPRT and AS52/XPRT), an in vitro cytogenetics assay using CHL cells, an unscheduled DNA synthesis assay and an in vivo micronucleus assay.

No adverse effects upon fertility were observed in male and female rats at oral doses up to 40 mg/kg pioglitazone daily prior to and throughout mating and gestation (approximately nine times the MRHD based on mg/m^2).

13.2 Animal Toxicology and/or Pharmacology

Heart enlargement has been observed in mice (100 mg/kg), rats (4 mg/kg and above) and dogs (3 mg/kg) treated orally with pioglitazone (approximately 11, one, and two times the MRHD for mice, rats and dogs, respectively, based on mg/m^2). In a one-year rat study, drug-related early death due to apparent heart dysfunction occurred at an oral dose of 160 mg/kg (approximately 35 times the MRHD based on mg/m^2). Heart enlargement was seen in a 13-week study in monkeys at oral doses of 8.9 mg/kg and above (approximately four times the MRHD based on mg/m^2), but not in a 52-week study at oral doses up to 32 mg/kg (approximately 13 times the MRHD based on mg/m^2).

14 CLINICAL STUDIES

The effectiveness of OSENI has been established based on four adequate and well-controlled Phase 3 trials of alogliptin and pioglitazone as adjunct to diet to improve glycemic control in adult patients with type 2 diabetes mellitus.

In patients with type 2 diabetes mellitus, treatment with alogliptin and pioglitazone produced clinically meaningful and statistically significant improvements in A1C compared to either alogliptin or pioglitazone alone. As is typical for trials of agents to treat type 2 diabetes mellitus, the mean reduction in A1C with alogliptin and pioglitazone appears to be related to the degree of A1C elevation at baseline.

Alogliptin and Pioglitazone Coadministration in Patients with Type 2 Diabetes Mellitus Inadequately Controlled on Diet and Exercise

In a 26-week, double-blind, active-controlled study, a total of 655 patients inadequately controlled on diet and exercise alone (mean baseline A1C=8.8%) were randomized to receive alogliptin 25 mg alone, pioglitazone 30 mg alone, alogliptin 12.5 mg with pioglitazone 30 mg or alogliptin 25 mg with pioglitazone 30 mg once daily. Coadministration of alogliptin 25 mg with pioglitazone 30 mg resulted in statistically significant improvements from baseline in A1C and FPG compared to either alogliptin 25 mg alone or to pioglitazone 30 mg alone (Table 10). Coadministration of alogliptin 25 mg with pioglitazone 30 mg once daily resulted in statistically significant reductions in fasting plasma glucose (FPG) starting from Week 2 through Week 26 compared to either alogliptin 25 mg or pioglitazone 30 mg alone. A total of 3% of patients receiving alogliptin 25 mg coadministered with pioglitazone 30 mg, 11% of those receiving alogliptin 25 mg alone, and 6% of those receiving pioglitazone 30 mg alone required glycemic rescue.

Improvements in A1C were not affected by gender, age or baseline BMI.

The mean increase in body weight was similar between pioglitazone alone and alogliptin when coadministered with pioglitazone.

Table 11. Glycemic Parameters at Week 26 in a Coadministration Study of Alogliptin and Pioglitazone in Patients Inadequately Controlled on Diet and Exercise [Intent-to-treat population using last observation carried forward]
 | Alogliptin 25 mg | Pioglitazone 30 mg | Alogliptin 25 mg + Pioglitazone 30 mg
A1C (%) | N=160 | N=153 | N=158
Baseline (mean) | 8.8 | 8.8 | 8.8
Change from Baseline (adjusted mean [Least squares means adjusted for treatment, geographic region and baseline value]) | -1 | -1.2 | -1.7
Difference from alogliptin 25 mg (adjusted mean with 95% confidence interval) |  |  | -0.8 [p˂0.01 compared to alogliptin 25 mg or pioglitazone 30 mg] (-1, -0.5)
Difference from pioglitazone 30 mg (adjusted mean with 95% confidence interval) |  |  | -0.6 (-0.8, -0.3)
% of Patients (n/N) achieving A1C ≤ 7% | 24% (40/164) | 34% (55/163) | 63% (103/164)
FPG (mg/dL) | N=162 | N=157 | N=162
Baseline (mean) | 189 | 189 | 185
Change from Baseline (adjusted mean) | -26 | -37 | -50
Difference from alogliptin 25 mg (adjusted mean with 95% confidence interval) |  |  | -25 (-34, -15)
Difference from pioglitazone 30 mg (adjusted mean with 95% confidence interval) |  |  | -13 (-22, -4)

Alogliptin and Pioglitazone Coadministration in Patients with Type 2 Diabetes Mellitus Inadequately Controlled on Metformin Alone

In the second 26-week, double-blind, placebo-controlled study, a total of 1554 patients already on metformin (mean baseline A1C=8.5%) were randomized to one of 12 double-blind treatment groups: placebo; 12.5 mg or 25 mg of alogliptin alone; 15 mg, 30 mg or 45 mg of pioglitazone alone; or 12.5 mg or 25 mg of alogliptin in combination with 15 mg, 30 mg or 45 mg of pioglitazone. Patients were maintained on a stable dose of metformin (median dose=1,700 mg) during the treatment period. Coadministration of alogliptin and pioglitazone provided statistically significant improvements in A1C and FPG compared to placebo, to alogliptin alone, or to pioglitazone alone when added to background metformin therapy (Table 11, Figure 3). A total of 4%, 5% or 2% of patients receiving alogliptin 25 mg with 15 mg, 30 mg or 45 mg pioglitazone, 33% of patients receiving placebo, 13% of patients receiving alogliptin 25 mg, and 10%, 15% or 9% of patients receiving pioglitazone 15 mg, 30 mg or 45 mg alone required glycemic rescue.

Improvements in A1C were not affected by gender, age or baseline BMI.

The mean increase in body weight was similar between pioglitazone alone and alogliptin when coadministered with pioglitazone.

Table 12. Glycemic Parameters at Week 26 for Alogliptin and Pioglitazone Alone and in Combination in Patients with Type 2 Diabetes Mellitus [Intent-to-treat population using last observation carried forward]
 | Placebo | Alogliptin 25 mg | Pioglitazone 15 mg | Pioglitazone 30 mg | Pioglitazone 45 mg | Alogliptin 25 mg + Pioglitazone 15 mg | Alogliptin 25 mg + Pioglitazone 30 mg | Alogliptin 25 mg + Pioglitazone 45 mg
A1C (%) | N=126 | N=123 | N=127 | N=123 | N=126 | N=127 | N=124 | N=126
Baseline (mean) | 8.5 | 8.6 | 8.5 | 8.5 | 8.5 | 8.5 | 8.5 | 8.6
Change from baseline (adjusted mean [Least squares means adjusted for treatment, geographic region metformin dose and baseline value] with 95% confidence interval) | -0.1 | -0.9 | -0.8 | -0.9 | -1 | -1.3 [p≤0.01 when compared to pioglitazone and alogliptin alone] | -1.4 | -1.6
Difference from pioglitazone (adjusted mean with 95% confidence interval) | - | - | - | - | - | -0.5(-0.7, -0.3) | -0.5(-0.7, -0.3) | -0.6(-0.8, -0.4)
Difference from alogliptin (adjusted mean with 95% confidence interval) | - | - | - | - | - | -0.4(-0.6, -0.1) | -0.5(-0.7, -0.3) | -0.7(-0.9, -0.5)
Patients (%) achieving A1C ≤7% | 6% (8/129) | 27% (35/129) | 26% (33/129) | 30% (38/129) | 36% (47/129) | 55% (71/130) | 53% (69/130) | 60% (78/130)
FPG (mg/dL) | N=129 | N=126 | N=127 | N=125 | N=129 | N=130 | N=126 | N=127
Baseline (mean) | 177 | 184 | 177 | 175 | 181 | 179 | 179 | 178
Change from baseline (adjusted mean with 95% confidence interval) | 7 | -19 | -24 | -29 | -32 | -38 | -42 | -53
Difference from pioglitazone (adjusted mean with 95% confidence interval) | - | - | - | - | - | -14(-24, -5) | -13(-23, -3) | -20(-30, -11)
Difference from alogliptin (adjusted mean with 95% confidence interval) | - | - | - | - | - | -19(-29, -10) | -23(-33, -13) | -34(-44, -24)

Figure 3. Change from Baseline in A1C at Week 26 with Alogliptin and Pioglitazone Alone and Alogliptin in Combination with Pioglitazone when Added to Metformin

Alogliptin Add-On Therapy in Patients with Type 2 Diabetes Mellitus Inadequately Controlled on Metformin in Combination with Pioglitazone

In a 52 week, active-comparator study, a total of 803 patients inadequately controlled (mean baseline A1C=8.2%) on a current regimen of pioglitazone 30 mg and metformin at least 1500 mg per day or at the maximum tolerated dose were randomized to either receive the addition of alogliptin 25 mg or the titration of pioglitazone 30 mg to 45 mg following a four week, single-blind, placebo run-in period. Patients were maintained on a stable dose of metformin (median dose=1700 mg). Patients who failed to meet prespecified hyperglycemic goals during the 52-week treatment period received glycemic rescue therapy.

In combination with pioglitazone and metformin, alogliptin 25 mg was shown to be statistically superior in lowering A1C and FPG compared with the titration of pioglitazone from 30 mg to 45 mg at Week 26 and Week 52 (Table 13, results shown only for Week 52). A total of 11% of patients who were receiving alogliptin 25 mg in combination with pioglitazone 30 mg and metformin and 22% of patients receiving a dose titration of pioglitazone from 30 mg to 45 mg in combination with metformin required glycemic rescue.

Improvements in A1C were not affected by gender, age, race or baseline BMI. The mean increase in body weight was similar in both treatment arms. Lipid effects were neutral.

Table 13. Glycemic Parameters at Week 52 in an Active-Controlled Study of Alogliptin as Add-On Combination Therapy to Metformin and Pioglitazone [Intent-to-treat population using last observation on study]
 | Alogliptin 25 mg + Pioglitazone 30 mg + Metformin | Pioglitazone 45 mg + Metformin
A1C (%) | N=397 | N=394
Baseline (mean) | 8.2 | 8.1
Change from Baseline (adjusted mean [Least squares means adjusted for treatment, baseline value, geographic region and baseline metformin dose]) | -0.7 | -0.3
Difference from Pioglitazone 45 mg + Metformin (adjusted mean with 95% confidence interval) | -0.4 [Noninferior and statistically superior to metformin plus pioglitazone at the 0.025 one-sided significance level] (-0.5, -0.3) | -
% of Patients (n/N) achieving A1C ≤7% | 33% (134/404) [p˂0.001 compared to pioglitazone 45 mg + metformin] | 21% (85/399)
FPG (mg/dL) | N=399 | N=396
Baseline (mean) | 162 | 162
Change from Baseline (adjusted mean) | -15 | -4
Difference from Pioglitazone 45 mg + Metformin (adjusted mean with 95% confidence interval) | -11 (-16, -6) | -

Alogliptin Add-On Therapy to a Thiazolidinedione

A 26-week, placebo-controlled study, was conducted to evaluate the efficacy and safety of alogliptin as add-on therapy to pioglitazone in patients with type 2 diabetes mellitus. A total of 493 patients inadequately controlled on a thiazolidinedione alone or in combination with metformin or a sulfonylurea (mean baseline A1C=8%) were randomized to receive alogliptin 12.5 mg, alogliptin 25 mg or placebo. Patients were maintained on a stable dose of pioglitazone (median dose=30 mg) during the treatment period and those who were also previously treated on metformin (median dose=2,000 mg) or sulfonylurea (median dose=10 mg) prior to randomization were maintained on the combination therapy during the treatment period. All patients entered into a four week, single-blind, placebo run-in period prior to randomization. Following randomization, all patients continued to receive instruction on diet and exercise. Patients who failed to meet prespecified hyperglycemic goals during the 26-week treatment period received glycemic rescue.

The addition of alogliptin 25 mg once daily to pioglitazone therapy resulted in significant improvements from baseline in A1C and FPG at Week 26 when compared to the addition of placebo (Table 14). A total of 9% of patients who were receiving alogliptin 25 mg and 12% of patients receiving placebo required glycemic rescue.

The improvement in A1C was not affected by gender, age, baseline BMI or baseline pioglitazone dose. The mean increase in body weight was similar between alogliptin and placebo when given in combination with pioglitazone. Lipid effects were neutral.

Table 14. Glycemic Parameters at Week 26 in a Placebo-Controlled Study of Alogliptin as Add-On Therapy to Pioglitazone [Intent-to-treat population using last observation on study]
 | Alogliptin 25 mg + Pioglitazone ± Metformin ± Sulfonylurea | Placebo + Pioglitazone ± Metformin ± Sulfonylurea
A1C (%) | N=195 | N=95
Baseline (mean) | 8 | 8
Change from baseline (adjusted mean [Least squares means adjusted for treatment, baseline value, geographic region, baseline treatment regimen (pioglitazone, pioglitazone + metformin or pioglitazone + sulfonylurea) and baseline pioglitazone dose]) | -0.8 | -0.2
Difference from placebo (adjusted mean with 95% confidence interval) | -0.6 [p˂0.01 compared to placebo] (-0.8, -0.4) | -
% of patients (n/N) achieving A1C ≤7% | 49% (98/199) | 34% (33/97)
FPG (mg/dL) | N=197 | N=97
Baseline (mean) | 170 | 172
Change from baseline (adjusted mean) | -20 | -6
Difference from placebo (adjusted mean with 95% confidence interval) | -14 (-23, -5) | -

Cardiovascular Safety Trial

A randomized, double-blind, placebo-controlled cardiovascular outcomes trial (EXAMINE) was conducted to evaluate the cardiovascular risk of alogliptin. The trial compared the risk of major adverse cardiovascular events (MACE) between alogliptin (N=2,701) and placebo (N=2,679) when added to standard of care therapies for diabetes and atherosclerotic vascular disease (ASCVD). The trial was event driven and patients were followed until a sufficient number of primary outcome events accrued.

Eligible patients were adults with type 2 diabetes mellitus who had inadequate glycemic control at baseline (e.g., HbA1c >6.5%) and had been hospitalized for an acute coronary syndrome event (e.g., acute myocardial infarction or unstable angina requiring hospitalization) 15 to 90 days prior to randomization. The dose of alogliptin was based on estimated renal function at baseline per dosage and administration recommendations [see Dosage and Administration (2.3)]. The average time between an acute coronary syndrome event and randomization was approximately 48 days.

The mean age of the population was 61 years. Most patients were male (68%), White (73%), and were recruited from outside of the U.S. (86%). Asian and Black or African American patients contributed 20% and 4% of the total population, respectively. At the time of randomization patients had a diagnosis of type 2 diabetes mellitus for approximately 9 years, 87% had a prior myocardial infarction and 14% were current smokers. Hypertension (83%) and renal impairment (27% with an eGFR ≤60 ml/min/1.73 m^2) were prevalent co-morbid conditions. Use of medications to treat diabetes (e.g., metformin 73%, sulfonylurea 54%, insulin 41%), and ASCVD (e.g., statin 94%, aspirin 93%, renin-angiotensin system blocker 88%, beta-blocker 87%) was similar between patients randomized to alogliptin and placebo at baseline. During the trial, medications to treat diabetes and ASCVD could be adjusted to ensure care for these conditions adhered to standard of care recommendations set by local practice guidelines.

The primary endpoint in EXAMINE was the time to first occurrence of a MACE defined as the composite of cardiovascular death, nonfatal myocardial infarction (MI), or nonfatal stroke. The study was designed to exclude a pre-specified risk margin of 1.3 for the hazard ratio of MACE. The median exposure to study drug was 526 days and 95% of the patients were followed to study completion or death.

Table 15 shows the study results for the primary MACE composite endpoint and the contribution of each component to the primary MACE endpoint. The upper bound of the confidence interval was 1.16 and excluded a risk margin larger than 1.3.

Table 15. Patients with MACE in EXAMINE
Composite of first event of CV death, nonfatal MI or nonfatal stroke (MACE) | Alogliptin |  | Placebo |  | Hazard Ratio
Composite of first event of CV death, nonfatal MI or nonfatal stroke (MACE) | Number of Patients (%) | Rate per 100 PY [Patient Years (PY)] | Number of Patients (%) | Rate per 100 PY | (98% CI)
Composite of first event of CV death, nonfatal MI or nonfatal stroke (MACE) |  | N=2,701 |  | N=2,679
Composite of first event of CV death, nonfatal MI or nonfatal stroke (MACE) |  | 305 (11.3) | 7.6 | 316 (11.8) | 7.9 | 0.96 (0.80, 1.16)
CV Death | 89 (3.3) | 2.2 | 111 (4.1) | 2.8
Nonfatal MI | 187 (6.9) | 4.6 | 173 (6.5) | 4.3
Nonfatal stroke | 29 (1.1) | 0.7 | 32 (1.2) | 0.8

The Kaplan-Meier based cumulative event probability is presented in Figure 4 for the time to first occurrence of the primary MACE composite endpoint by treatment arm. The curves for placebo and alogliptin overlap throughout the duration of the study. The observed incidence of MACE was highest within the first 60 days after randomization in both treatment arms (14.8 MACE per 100 PY), decreased from day 60 to the end of the first year (8.4 per 100 PY) and was lowest after one year of follow-up (5.2 per 100 PY).

Figure 4. Observed Cumulative Rate of MACE in EXAMINE

The rate of all cause death was similar between treatment arms with 153 (3.6 per 100 PY) recorded among patients randomized to alogliptin and 173 (4.1 per 100 PY) among patients randomized to placebo. A total of 112 deaths (2.9 per 100 PY) among patients on alogliptin and 130 among patients on placebo (3.5 per 100 PY) were adjudicated as cardiovascular deaths.

16 HOW SUPPLIED/STORAGE AND HANDLING

OSENI tablets are available in the following strengths and packages:

25 mg/15 mg tablet: yellow, round, biconvex and film-coated with both “A/P” and “25/15” printed on one side, available in:

NDC 64764-251-03 | Bottles of 30 tablets
NDC 64764-251-04 | Bottles of 90 tablets
NDC 64764-251-05 | Bottles of 500 tablets

25 mg/30 mg tablet: peach, round, biconvex and film-coated with both “A/P” and “25/30” printed on one side, available in:

NDC 64764-253-03 | Bottles of 30 tablets
NDC 64764-253-04 | Bottles of 90 tablets
NDC 64764-253-05 | Bottles of 500 tablets

25 mg/45 mg tablet: red, round, biconvex, film-coated and with both “A/P” and “25/45” printed on one side, available in:

NDC 64764-254-03 | Bottles of 30 tablets
NDC 64764-254-04 | Bottles of 90 tablets
NDC 64764-254-05 | Bottles of 500 tablets

12.5 mg/30 mg tablet: pale peach, round, biconvex and film-coated with both “A/P” and “12.5/30” printed on one side, available in:

NDC 64764-123-03 | Bottles of 30 tablets
NDC 64764-123-04 | Bottles of 90 tablets
NDC 64764-123-05 | Bottles of 500 tablets

Storage

Store at 25°C (77°F); excursions permitted to 15° to 30°C (59° to 86°F) [see USP Controlled Room Temperature]. Keep container tightly closed and protect from moisture and humidity.

17 PATIENT COUNSELING INFORMATION

Advise the patient to read the FDA-approved patient labeling (Medication Guide).

- Congestive Heart Failure: Inform patients of the signs and symptoms of heart failure. Instruct patients who experience an unusually rapid increase in weight or edema, shortness of breath, or other symptoms of heart failure while on OSENI to immediately report these symptoms to their healthcare provider [see Warnings and Precautions (5.1)].
- Pancreatitis: Inform patients that acute pancreatitis has been reported during use of OSENI. Educate patients that persistent, severe abdominal pain, sometimes radiating to the back, which may or may not be accompanied by vomiting, is the hallmark symptom of acute pancreatitis. Instruct patients to promptly discontinue OSENI and contact their healthcare provider if persistent severe abdominal pain occurs [see Warnings and Precautions (5.2)].
- Hypersensitivity Reactions: Inform patients that allergic reactions have been reported during use of OSENI. Instruct patients if symptoms of allergic reactions (including skin rash, hives and swelling of the face, lips, tongue and throat that may cause difficulty in breathing or swallowing) occur, patients should discontinue OSENI and seek medical advice promptly [see Warnings and Precautions (5.3)].
- Hepatic Effects: Instruct patients to promptly stop taking OSENI and seek immediate medical advice if they experience signs or symptoms of liver injury (e.g., unexplained nausea, vomiting, abdominal pain, fatigue, anorexia or dark urine) [see Warnings and Precautions (5.4)].
- Edema: Inform patients that OSENI use can lead to new-onset or worsening of edema. Instruct patients to immediately report symptoms of rapid weight increase or worsening edema to their healthcare provider [see Warnings and Precautions (5.5)].
- Fractures: Inform female patients about the risk of fractures while taking OSENI. Provide them with information on factors that may contribute to fracture risk [see Warnings and Precautions (5.6)].
- Urinary Bladder Tumors: Advise patients to promptly report any hematuria, dysuria, or urinary urgency that develops or increases during treatment, as these may be due to bladder cancer [see Warnings and Precautions (5.7)].
- Hypoglycemia with Concomitant Use with Insulin or Insulin Secretagogues: Inform patients that the risk of hypoglycemia is increased when OSENI is used with insulin or insulin secretagogues (such as a sulfonylurea). Educate patients on the signs and symptoms of hypoglycemia [see Warnings and Precautions (5.8)].
- Macular Edema: Educate patients on the signs and symptoms of macular edema and advise them to seek medical attention from an ophthalmologist if they experience symptoms of macular edema [see Warnings and Precautions (5.9)].
- Severe and Disabling Arthralgia: Inform patients that severe and disabling joint pain may occur with OSENI. The time to onset of symptoms can range from one day to years. Instruct patients to seek medical advice if severe joint pain occurs [see Warnings and Precautions (5.10)].
- Bullous Pemphigoid: Inform patients that bullous pemphigoid may occur with this OSENI. Instruct patients to seek medical advice if blisters or erosions occur [see Warnings and Precautions (5.11)].
- Females of Reproductive Age: Inform female patients that treatment with OSENI may result in an unintended pregnancy in some premenopausal anovulatory females due to its effect on ovulation [see Use in Specific Populations (8.3)].
- Dosage and Administration: Instruct patients to take OSENI with or without meals. Instruct patients if a dose is missed, not to double their next dose. Instruct patients that the tablets must never be split.

Distributed by:
Takeda Pharmaceuticals America, Inc.
Cambridge, MA 02142

OSENI, NESINA and ACTOS are registered trademarks of Takeda Pharmaceutical Company Limited.

©2025 Takeda Pharmaceuticals America, Inc. All rights reserved.

ALP008 R13

MEDICATION GUIDE
OSENI® (OH-senn-ee)
(alogliptin and pioglitazone)
tablets

Read this Medication Guide carefully before you start taking OSENI and each time you get a refill. There may be new information. This information does not take the place of talking with your healthcare provider about your medical condition or your treatment. If you have any questions about OSENI, ask your healthcare provider or pharmacist.

What is the most important information I should know about OSENI?
OSENI can cause serious side effects, including:

1. Heart failure: OSENI can cause heart failure and cause your body to keep extra fluid (fluid retention), which leads to swelling (edema) and weight gain. Extra body fluid can make some heart problems worse or lead to heart failure. Heart failure means your heart does not pump blood well enough.
  Before you start taking OSENI:
  Tell your healthcare provider if you have ever had heart failure or have problems with your kidneys.
  Call your healthcare provider right away if you have any of the following symptoms:
  - increasing shortness of breath or trouble breathing, especially when you lie down
  - an unusually fast increase in weight
  - swelling or fluid retention, especially in the feet, ankles, or legs
  - unusual tiredness
  These may be symptoms of heart failure.
2. Inflammation of the pancreas (pancreatitis): Alogliptin, one of the medicines in OSENI, may cause pancreatitis, which may be severe. Certain medical conditions make you more likely to get pancreatitis.

Before you start taking OSENI:
Tell your healthcare provider if you have ever had:

- pancreatitis
- high blood triglyceride levels

- kidney problems
- stones in your gallbladder (gall stones)

- liver problems
- a history of alcoholism

Stop taking OSENI and call your healthcare provider right away if you have pain in your stomach area (abdomen) that is severe and will not go away. The pain may be felt going from your abdomen through to your back. The pain may happen with or without vomiting. These may be symptoms of pancreatitis.

What is OSENI?

- OSENI is a prescription medicine that contains 2 diabetes medicines, alogliptin (NESINA®) and pioglitazone (ACTOS®).
- OSENI is used along with diet and exercise to improve blood sugar (glucose) control in adults with type 2 diabetes.
- OSENI is not for people with type 1 diabetes.

It is not known if OSENI is safe and effective in children under the age of 18. OSENI is not recommended for use in children.

Who should not take OSENI?
Do not take OSENI if you:

- have severe heart failure
- are allergic to alogliptin (NESINA), pioglitazone (ACTOS) or any ingredient in OSENI or have had a serious allergic (hypersensitivity) reaction to alogliptin or pioglitazone. See the end of this Medication Guide for a complete list of the ingredients in OSENI.

Symptoms of a serious allergic reaction to OSENI may include:

- swelling of your face, lips, throat and other areas on your skin
- raised, red areas on your skin (hives)

- difficulty with swallowing or breathing
- skin rash, itching, flaking or peeling

If you have these symptoms, stop taking OSENI and contact your healthcare provider or go to the nearest hospital emergency room right away.

What should I tell my healthcare provider before and during treatment with OSENI?
Before you start taking OSENI, tell your healthcare provider if you:

- have heart failure
- have a type of diabetic eye disease that causes swelling of the back of the eye (macular edema)
- have kidney or liver problems
- have or have had inflammation of the pancreas (pancreatitis)
- have or have had cancer of the bladder
- are pregnant or plan to become pregnant. It is not known if OSENI can harm your unborn baby. Talk to your healthcare provider about the best way to control your blood sugar while you are pregnant or if you plan to become pregnant.
- are a premenopausal woman who does not have periods regularly or at all. OSENI may increase your chance of becoming pregnant. Talk to your healthcare provider about birth control choices while taking OSENI. Tell your healthcare provider right away if you become pregnant while taking OSENI.
- are breastfeeding or plan to breastfeed. It is not known if OSENI passes into your breast milk and if it can harm your baby. Talk with your healthcare provider about the best way to control your blood glucose levels while breastfeeding.

Tell your healthcare provider about all the medicines you take, including prescription and over-the-counter medicines, vitamins and herbal supplements.
Know the medicines you take. Keep a list of them and show it to your healthcare provider before you start a new medicine.
OSENI may affect the way other medicines work, and other medicines may affect how OSENI works. Contact your healthcare provider before you start or stop other types of medicines.

How should I take OSENI?

- Take OSENI exactly as your healthcare provider tells you to take it.
- Take OSENI 1 time each day with or without food.
- Do not break or cut OSENI tablets before swallowing.
- Your healthcare provider may need to change your dose of OSENI to control your blood glucose. Do not change your dose unless told to do so by your healthcare provider.
- If you miss a dose, take it as soon as you remember. If you do not remember until it is time for your next dose, skip the missed dose and take the next dose at your regular time. Do not take 2 doses of OSENI at the same time.
- If you take too much OSENI, call your healthcare provider or the Poison Help Line right away at 1-800-222-1222.
- If your body is under stress, such as from fever, infection, accident or surgery, the dose of your diabetes medicines may need to be changed. Call your healthcare provider right away.
- Stay on your diet and exercise programs and check your blood sugar as your healthcare provider tells you to.
- Your healthcare provider may do certain blood tests before you start OSENI and during treatment as needed. Your healthcare provider may change your dose of OSENI based on the results of your blood tests due to how well your kidneys are working.
- Your healthcare provider will check your diabetes with regular blood tests, including your blood sugar levels and your hemoglobin A1C.
- Your healthcare provider should check your eyes regularly while you take OSENI.

What are the possible side effects of OSENI?
OSENI can cause serious side effects, including:

- See “What is the most important information I should know about OSENI?”
- Serious allergic (hypersensitivity) reactions, such as:

- swelling of your face, lips, throat and other areas on your skin
- raised, red areas on your skin (hives)

- difficulty swallowing or breathing
- skin rash, itching, flaking or peeling

If you have these symptoms, stop taking OSENI and contact your healthcare provider right away or go to the nearest hospital emergency room

- Liver problems. Call your healthcare provider right away or go to the nearest hospital emergency room if you have unexplained symptoms such as:

- nausea or vomiting
- loss of appetite

- stomach pain
- dark urine

- unusual or unexplained tiredness
- yellowing of your skin or the whites of your eyes

- Broken bones (fractures). Usually in the hand, upper arm or foot in women. Talk to your healthcare provider for advice on how to keep your bones healthy.
- Bladder tumors. There may be an increased chance of having bladder cancer when you take OSENI. You should not take OSENI if you are receiving treatment for bladder cancer. Tell your healthcare provider right away if you have any of the following symptoms of bladder cancer:

- blood or a red color in your urine

- an increased need to urinate

- pain while you urinate

- Low blood sugar (hypoglycemia). If you take OSENI with another medicine that can cause low blood sugar, such as a sulfonylurea or insulin, your risk of getting low blood sugar is higher. The dose of your sulfonylurea medicine or insulin may need to be lowered while you take OSENI. Signs and symptoms of low blood sugar may include:

- shaking or feeling jittery
- change in vision
- change in mood

- sweating
- headache
- confusion

- fast heartbeat
- hunger
- dizziness

- Diabetic eye disease with swelling in the back of the eye (macular edema). Tell your healthcare provider right away if you have any changes in your vision. Your healthcare provider should check your eyes regularly.
- Release of an egg from an ovary in a woman (ovulation) leading to pregnancy. Ovulation may happen when premenopausal women who do not have regular monthly periods take OSENI. This can increase your chance of getting pregnant.
- Joint pain. Some people who take medicines called DPP-4 inhibitors, one of the medicines in OSENI, may develop joint pain that can be severe. Call your healthcare provider if you have severe joint pain.
- Skin reaction. Some people who take medicines called DPP-4 inhibitors, one of the medicines in OSENI, may develop a skin reaction called bullous pemphigoid that can require treatment in a hospital. Tell your healthcare provider right away if you develop blisters or the breakdown of the outer layer of your skin (erosion). Your healthcare provider may tell you to stop taking OSENI.

The most common side effects of OSENI include stuffy or runny nose and sore throat, back pain, cold-like symptoms (upper respiratory tract infection).
Tell your healthcare provider if you have any side effect that bothers you or that does not go away.
These are not all the possible side effects of OSENI. For more information, ask your healthcare provider or pharmacist.
Call your doctor for medical advice about side effects. You may report side effects to FDA at 1-800-FDA-1088.

How should I store OSENI?

- Store OSENI at room temperature between 68°F to 77°F (20°C to 25°C).
- Keep container tightly closed and protect from moisture and humidity.

Keep OSENI and all medicines out of the reach of children.

General information about the safe and effective use of OSENI
Medicines are sometimes prescribed for purposes other than those listed in the Medication Guide. Do not take OSENI for a condition for which it was not prescribed. Do not give OSENI to other people, even if they have the same symptoms you have. It may harm them.
You can ask your healthcare provider or pharmacist for information about OSENI that is written for health professionals.
For more information, go to www.oseni.com or call 1-877-TAKEDA-7 (1-877-825-3327).

What are the ingredients in OSENI?
Active Ingredients: alogliptin and pioglitazone
Inactive Ingredients: croscarmellose sodium, hydroxypropyl cellulose, lactose monohydrate, magnesium stearate, mannitol, and microcrystalline cellulose; the tablets are film-coated with ferric oxide (yellow and/or red), hypromellose, polyethylene glycol, talc, titanium dioxide, and are marked with printing ink (Red A1 or Gray F1).
Distributed by:
Takeda Pharmaceuticals America, Inc.
Cambridge, MA 02142
OSENI, NESINA and ACTOS are registered trademarks of Takeda Pharmaceutical Company Limited.
©2025 Takeda Pharmaceuticals America, Inc. All rights reserved.
ALP008 R13

This Medication Guide has been approved by the U.S. Food and Drug Administration.

2/2025

PACKAGE LABEL

PRINCIPAL DISPLAY PANEL - 12.5 mg/30 mg Tablet Bottle Label

NDC 64764-123-03

Oseni®
(alogliptin and
pioglitazone) tablets

12.5 mg/30 mg

Rx Only

Dispense with
Medication Guide

Takeda

30 Tablets

PACKAGE LABEL

PRINCIPAL DISPLAY PANEL - 25 mg/15 mg Tablet Bottle Label

NDC 64764-251-03

Oseni®
(alogliptin and
pioglitazone) tablets

25 mg/15 mg

Rx Only

Dispense with
Medication Guide

Takeda

30 Tablets

PACKAGE LABEL

PRINCIPAL DISPLAY PANEL - 25 mg/45 mg Tablet Bottle Label

NDC 64764-254-03

Oseni®
(alogliptin and
pioglitazone) tablets

25 mg/45 mg

Rx Only

Dispense with
Medication Guide

Takeda

30 Tablets

PACKAGE LABEL

PRINCIPAL DISPLAY PANEL - 25 mg/30 mg Tablet Bottle Label

NDC 64764-253-03

Oseni®
(alogliptin and
pioglitazone) tablets

25 mg/30 mg

Rx Only

Dispense with
Medication Guide

Takeda

30 Tablets